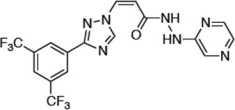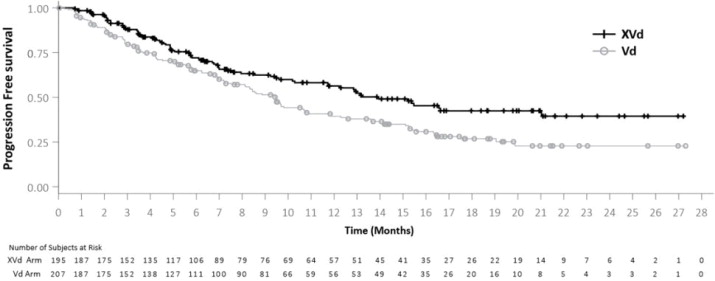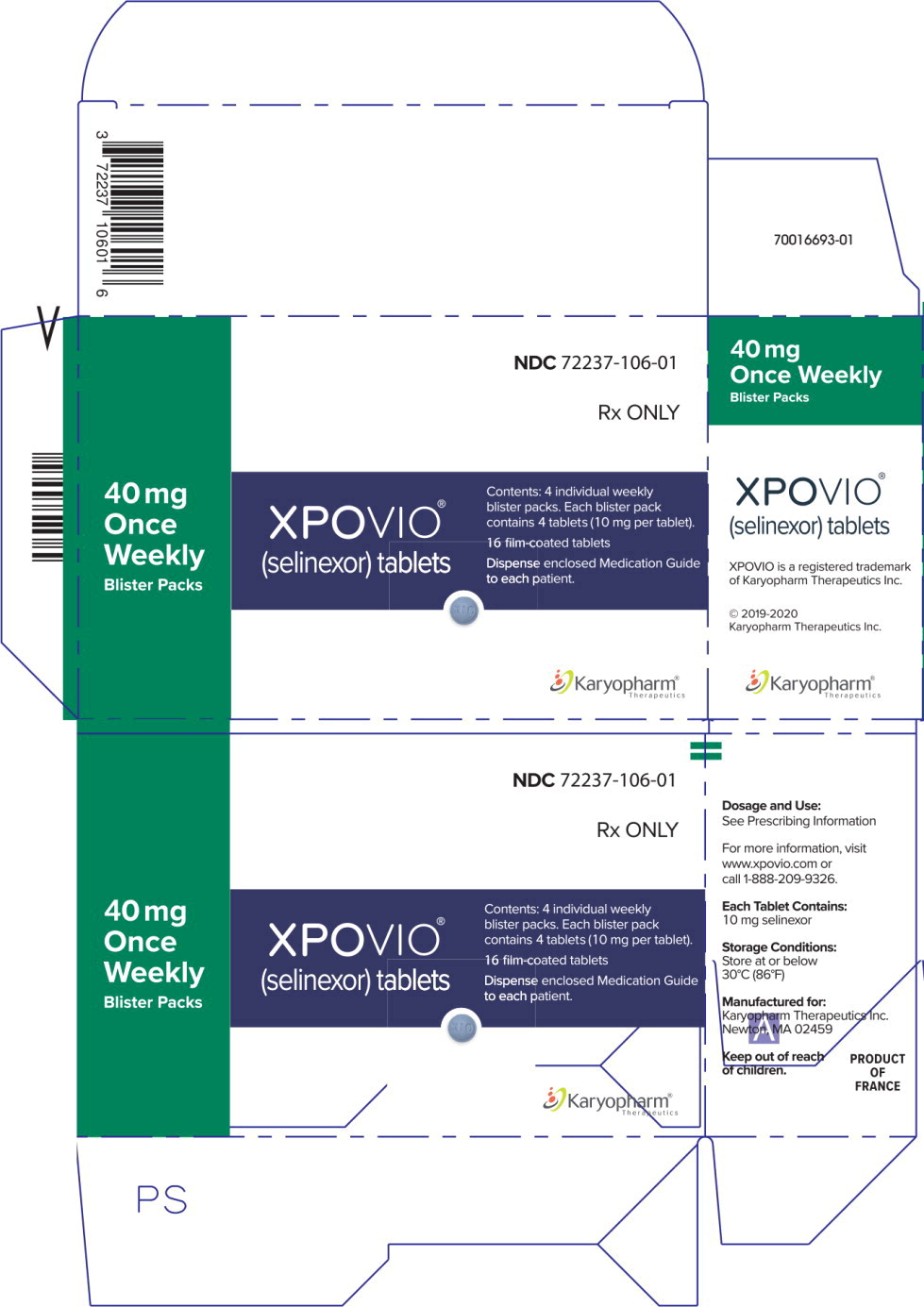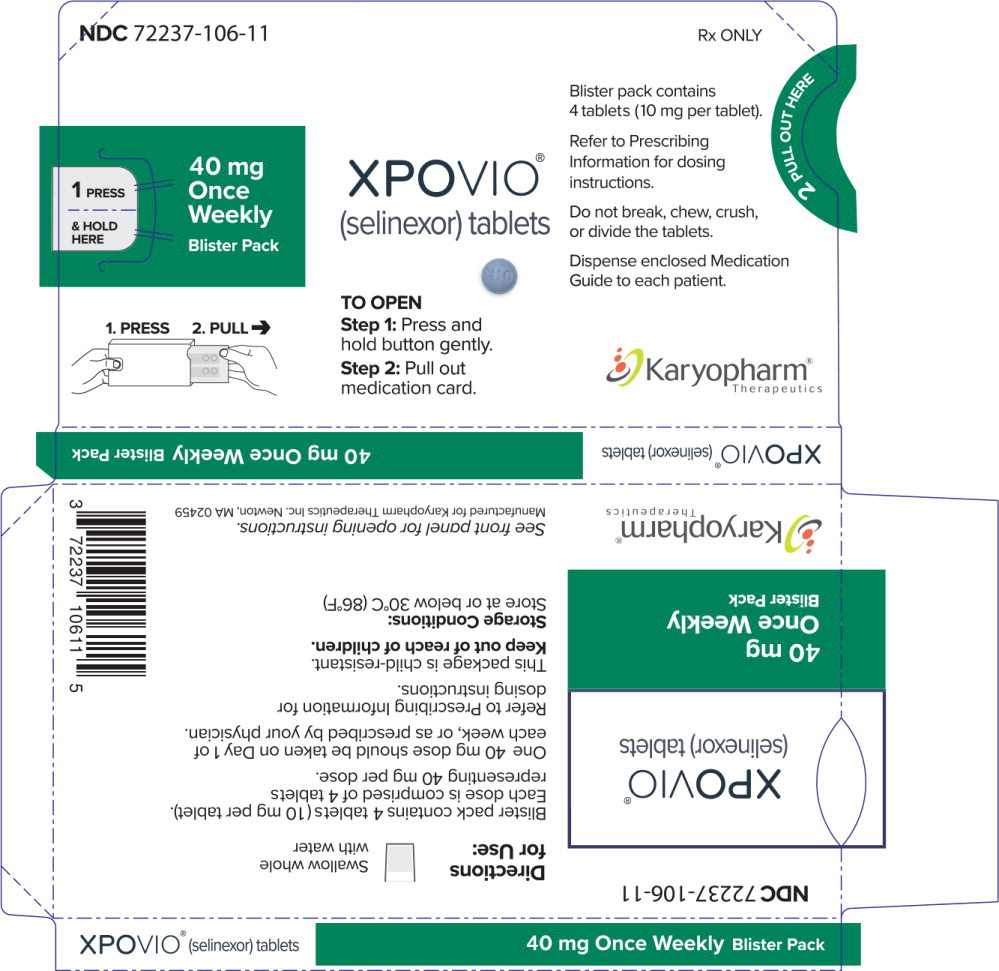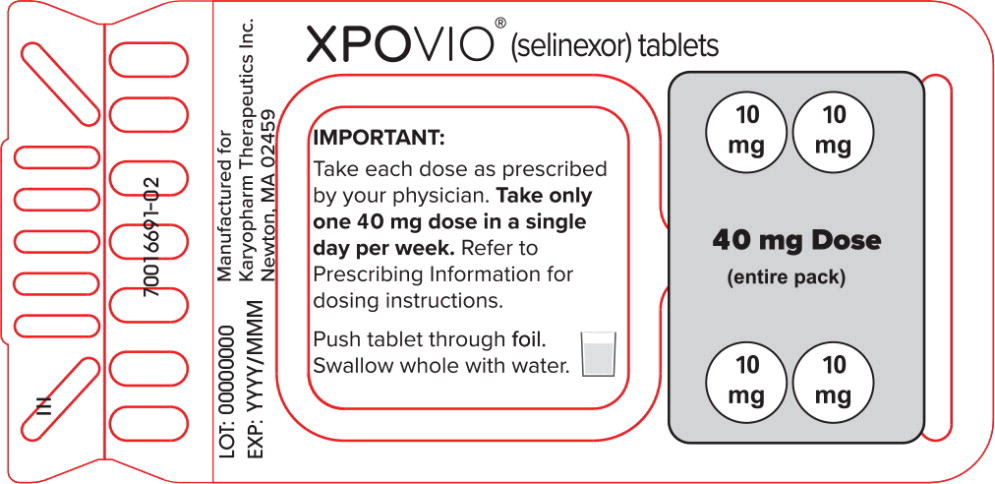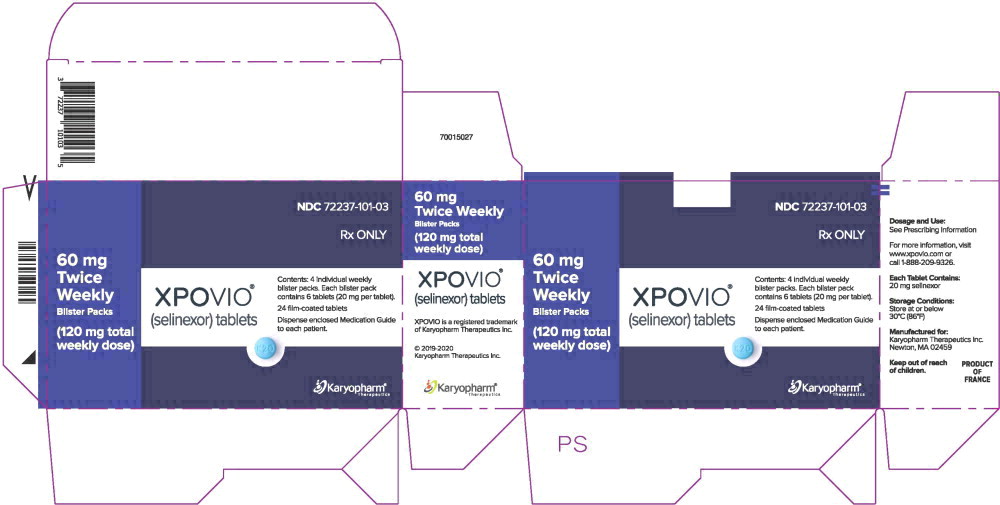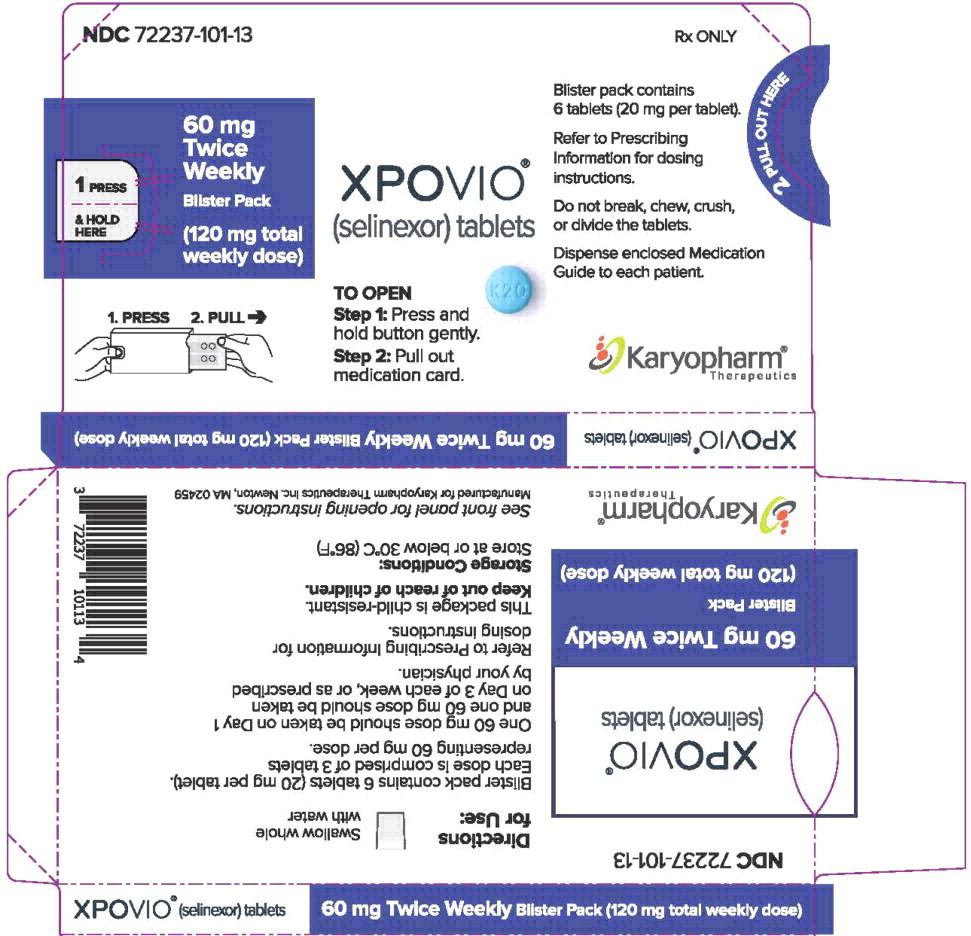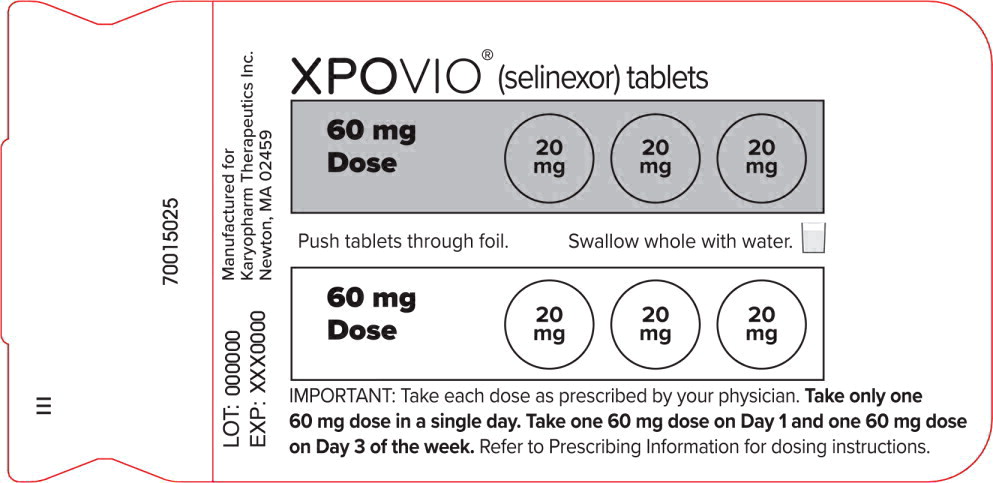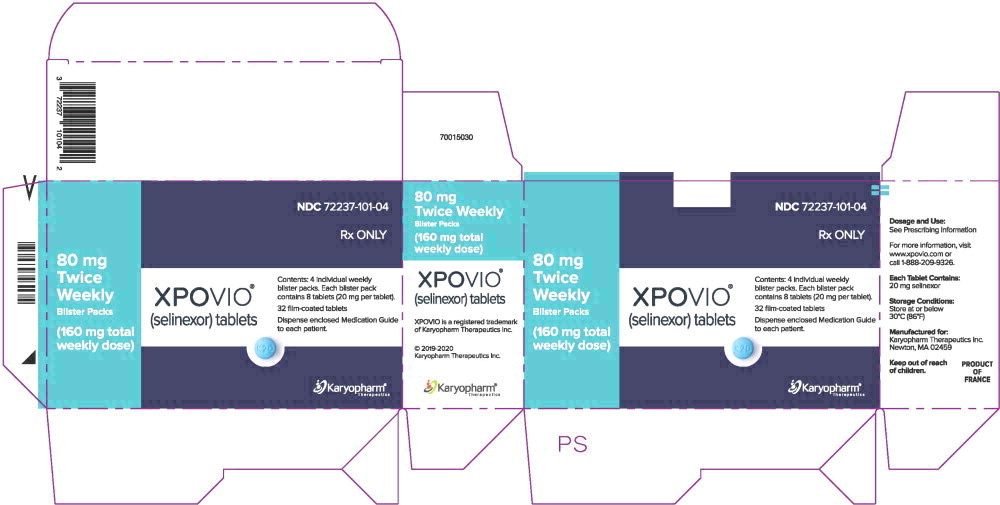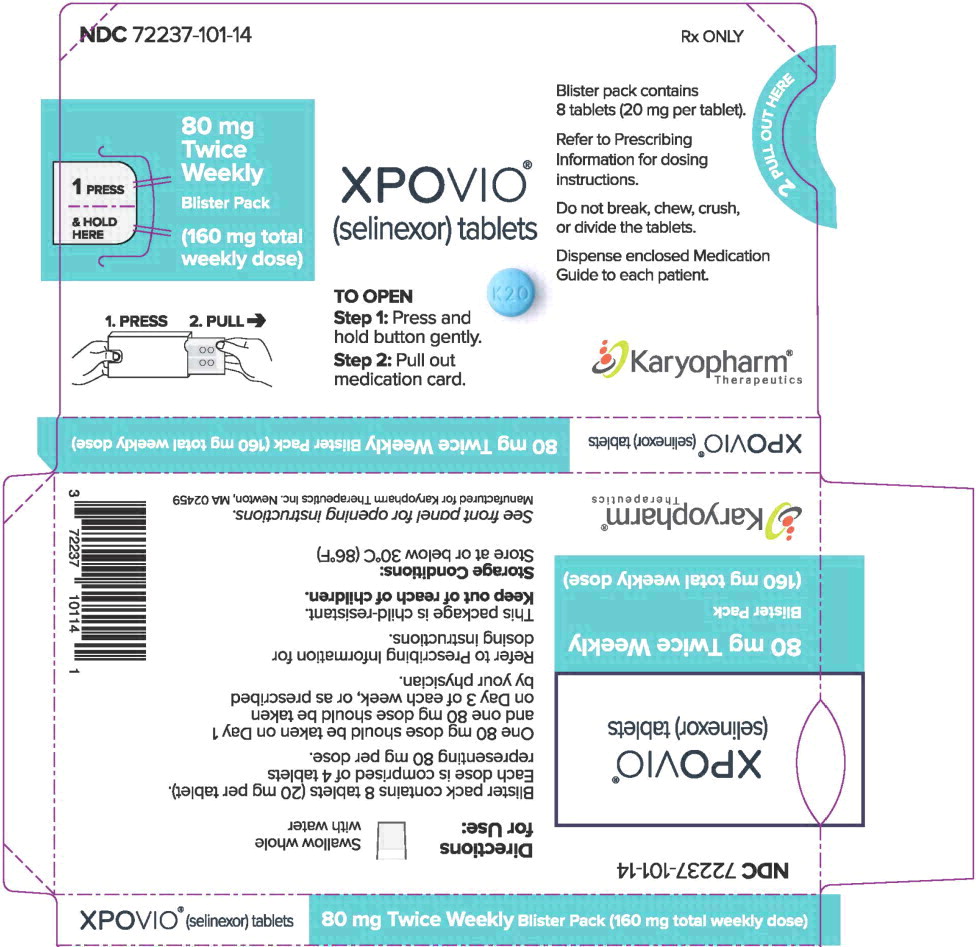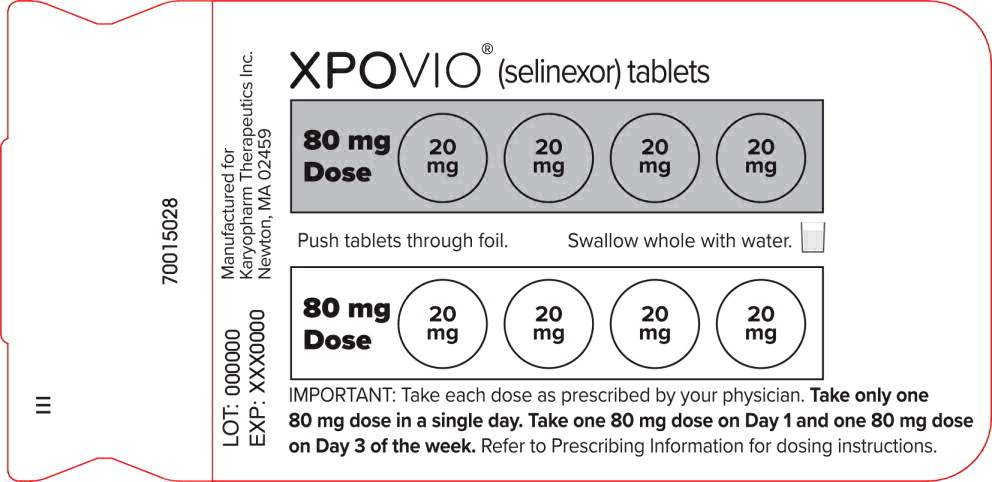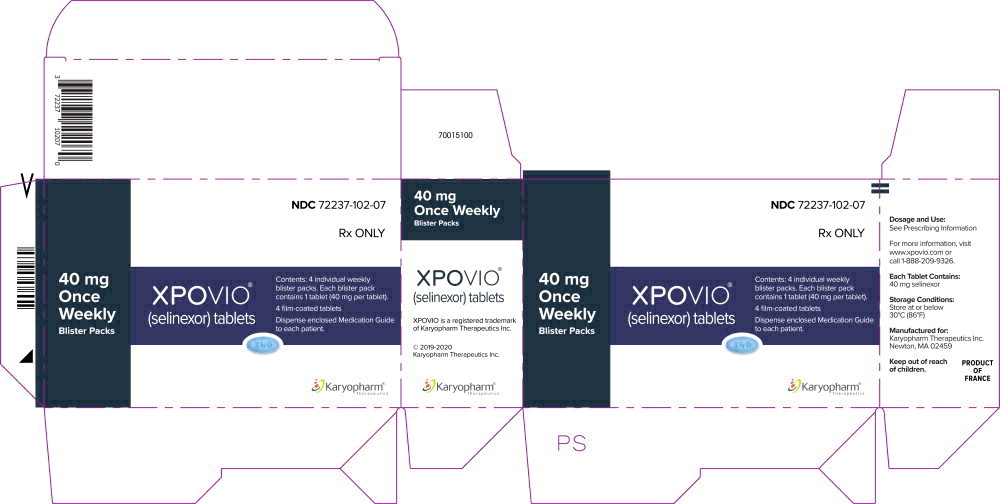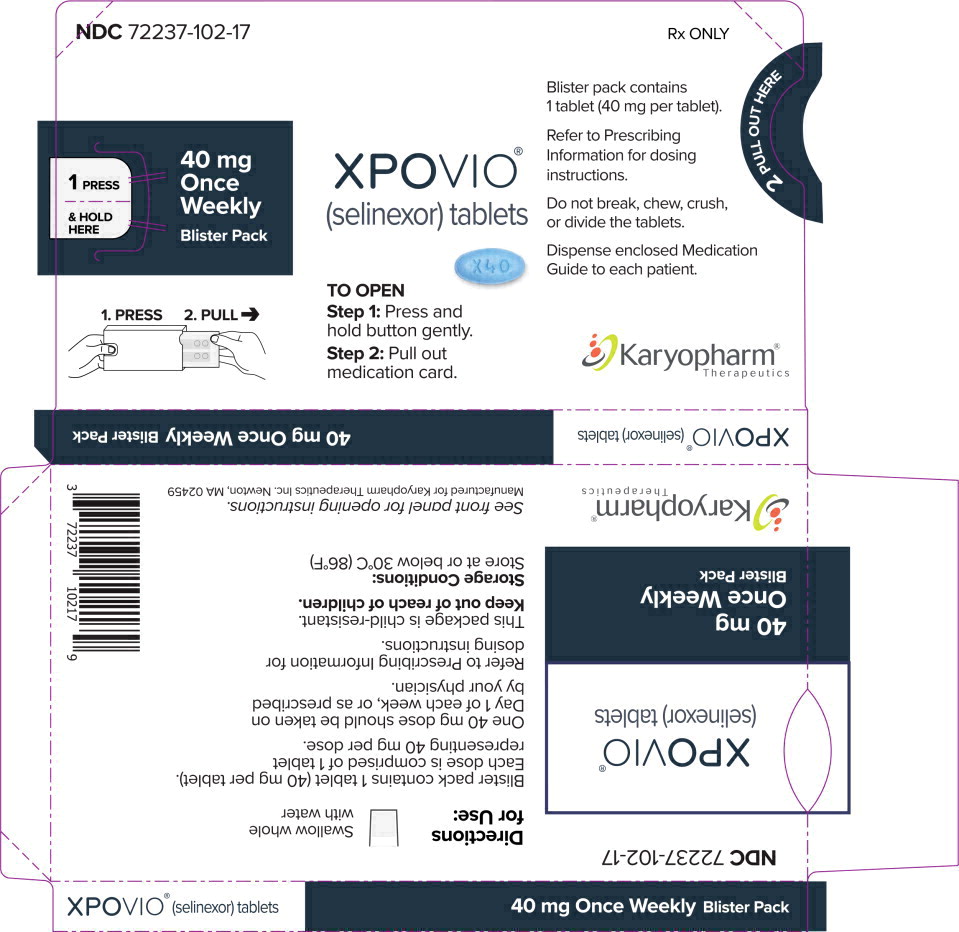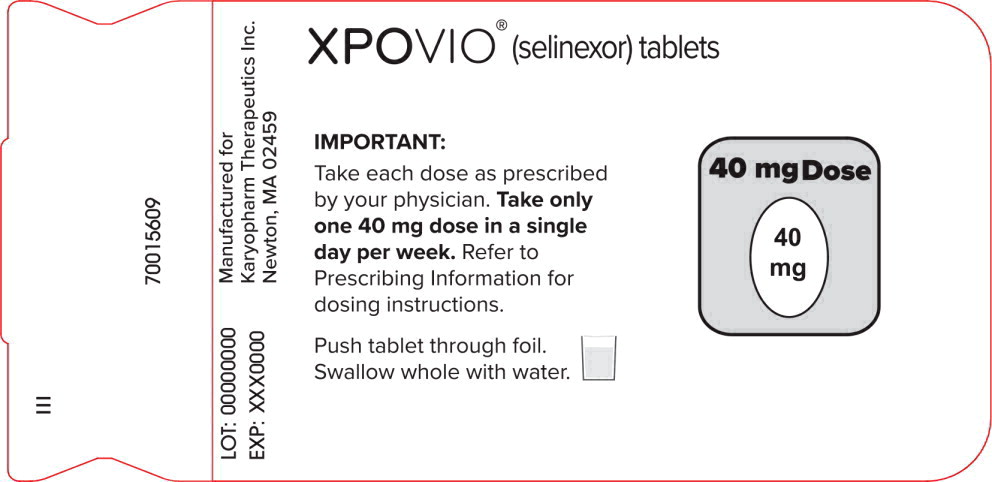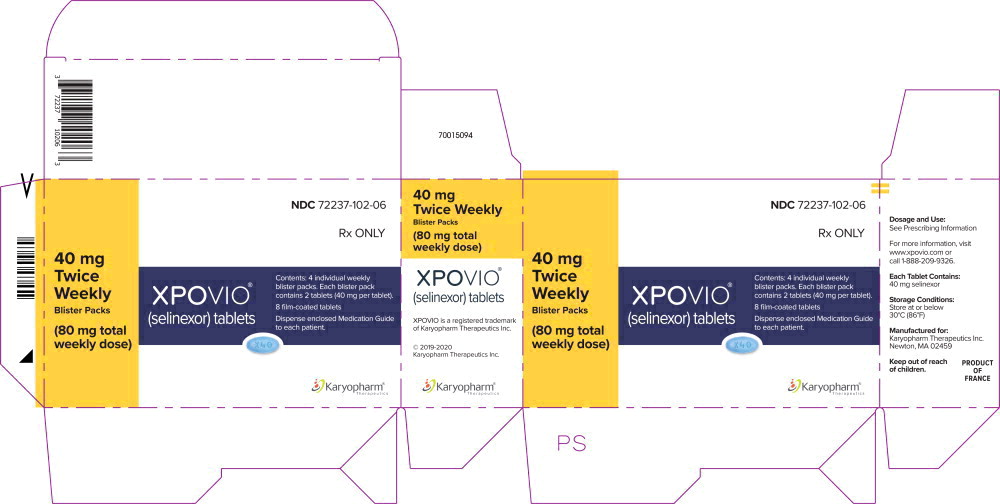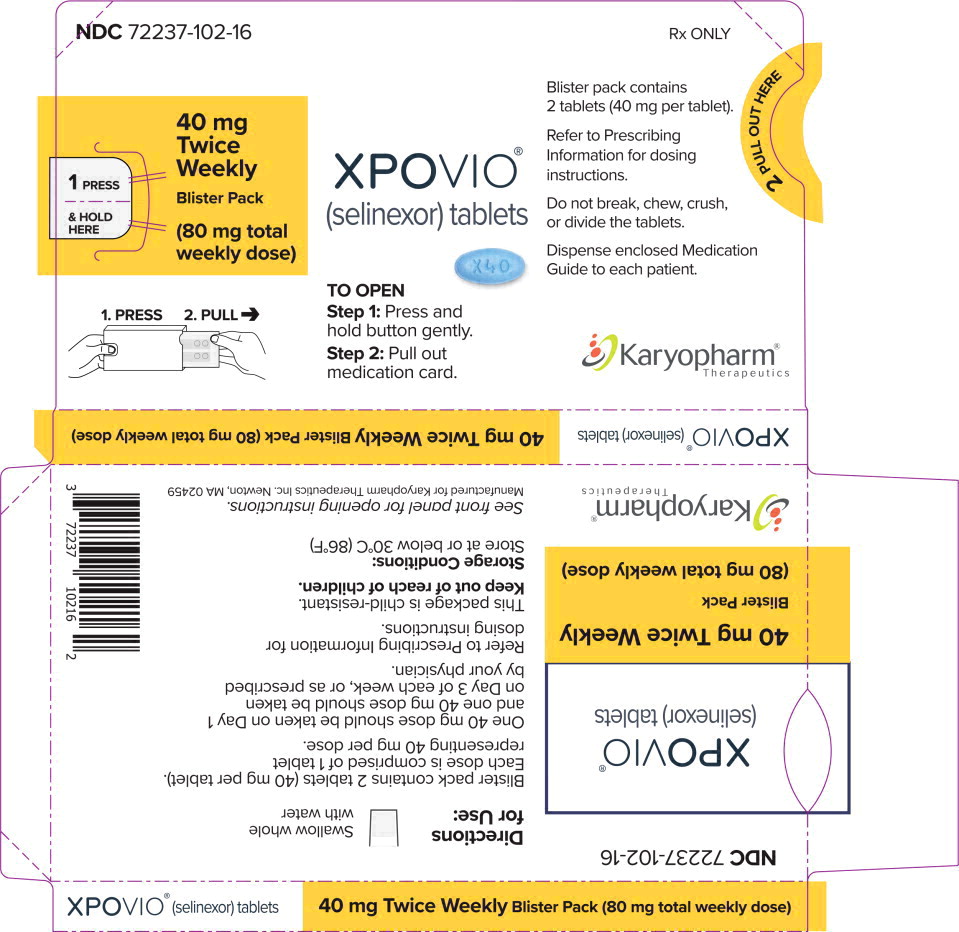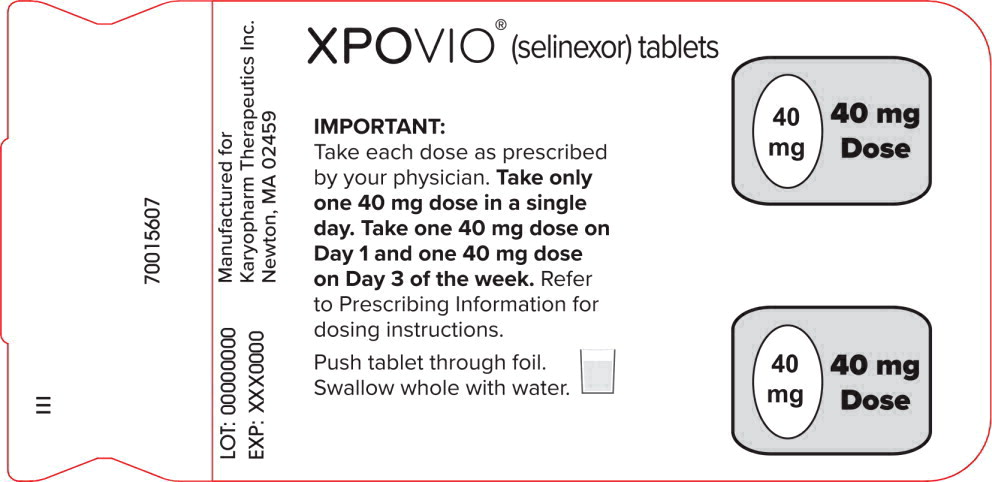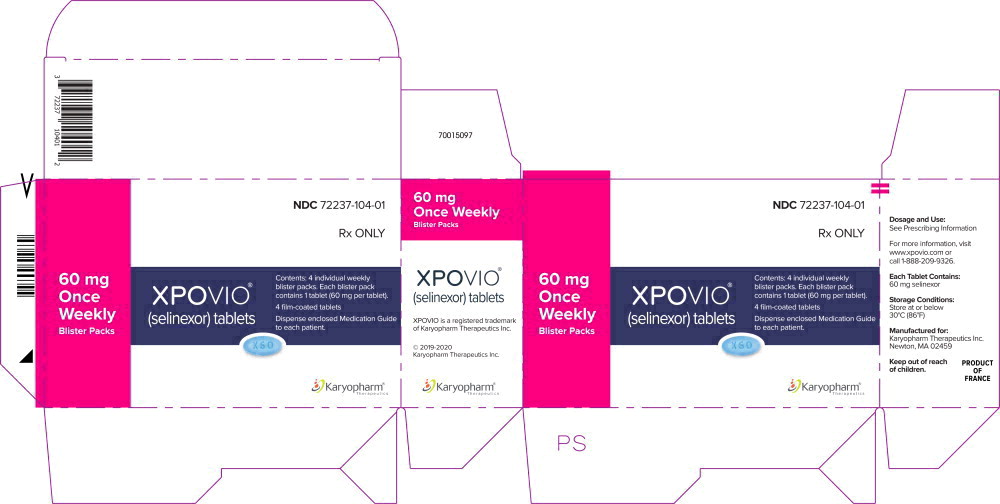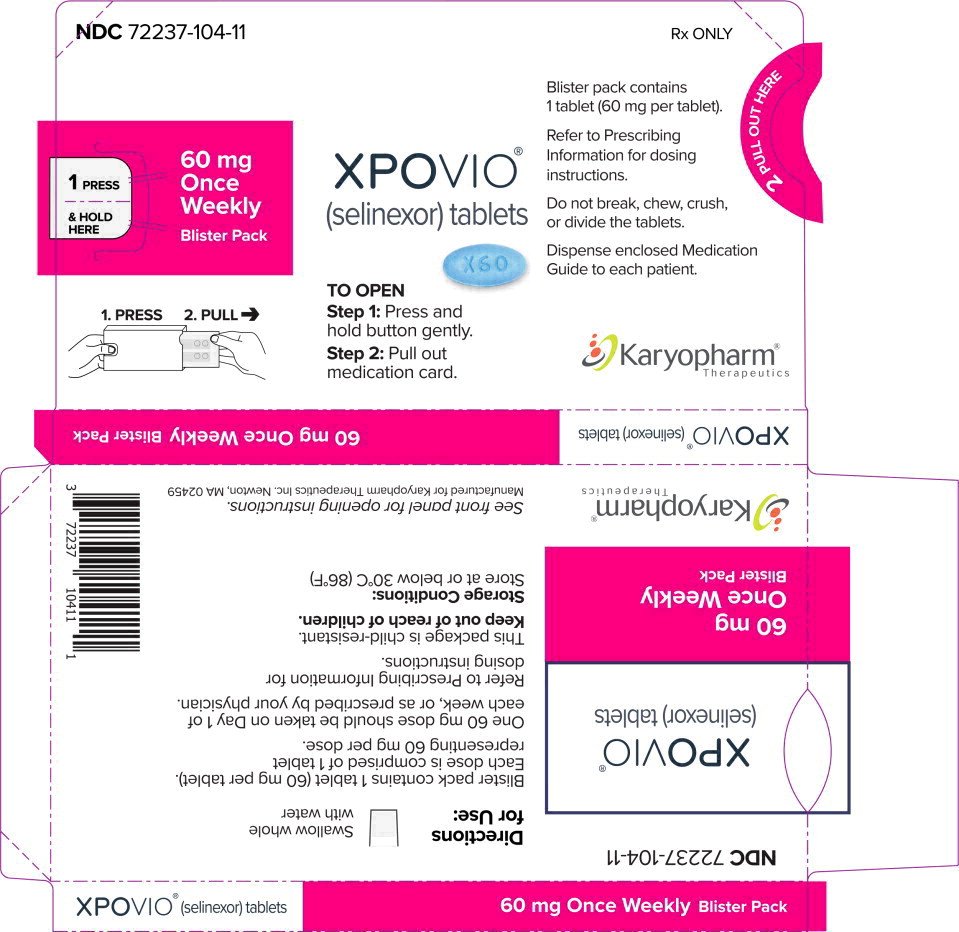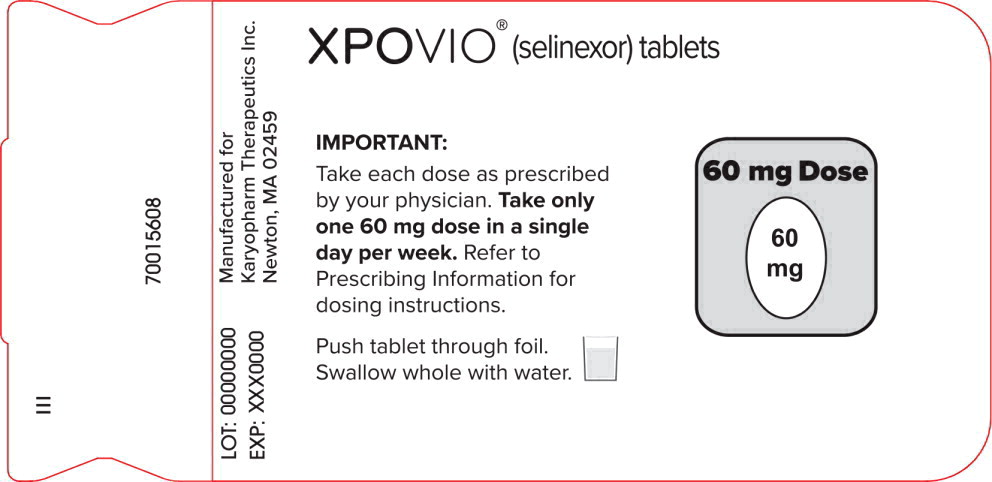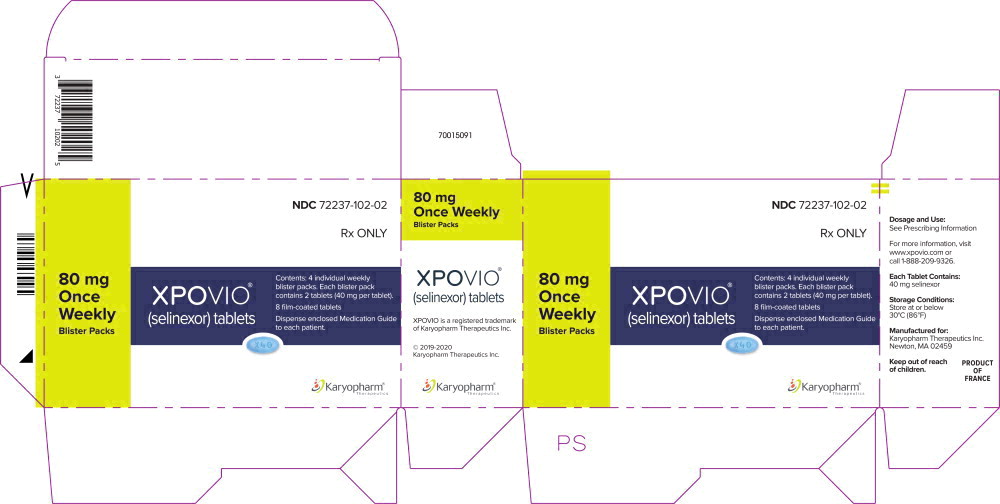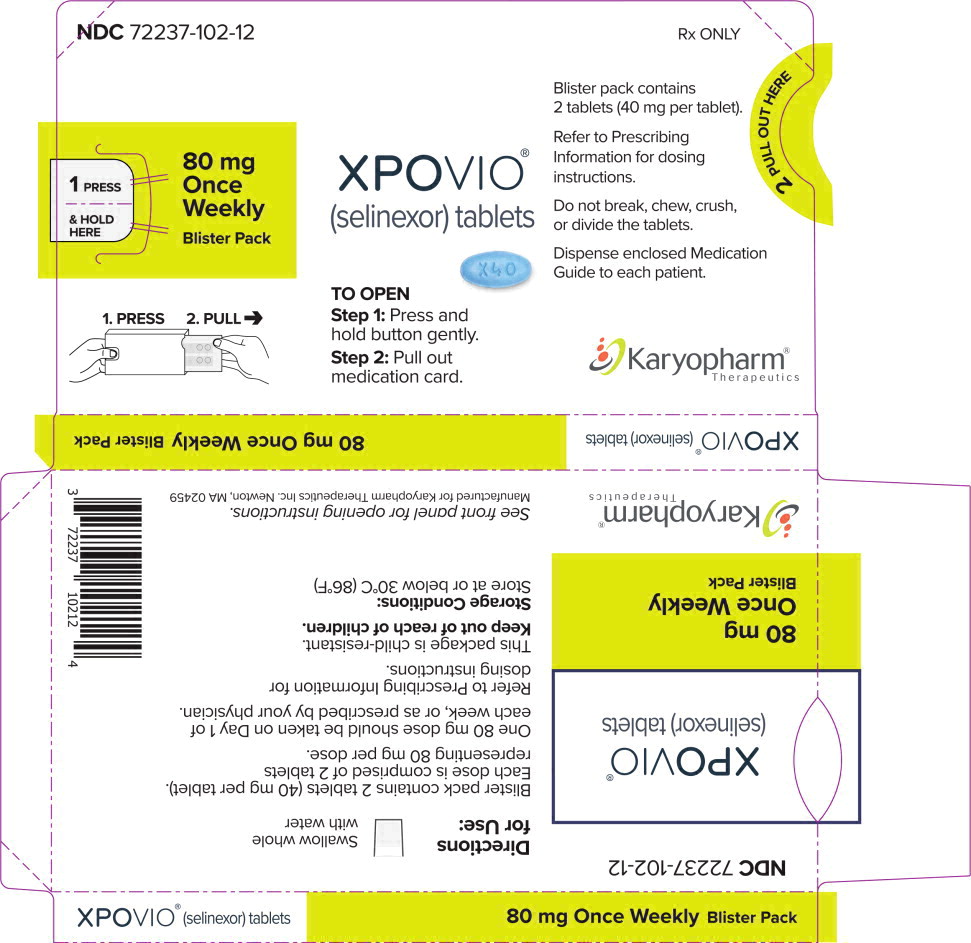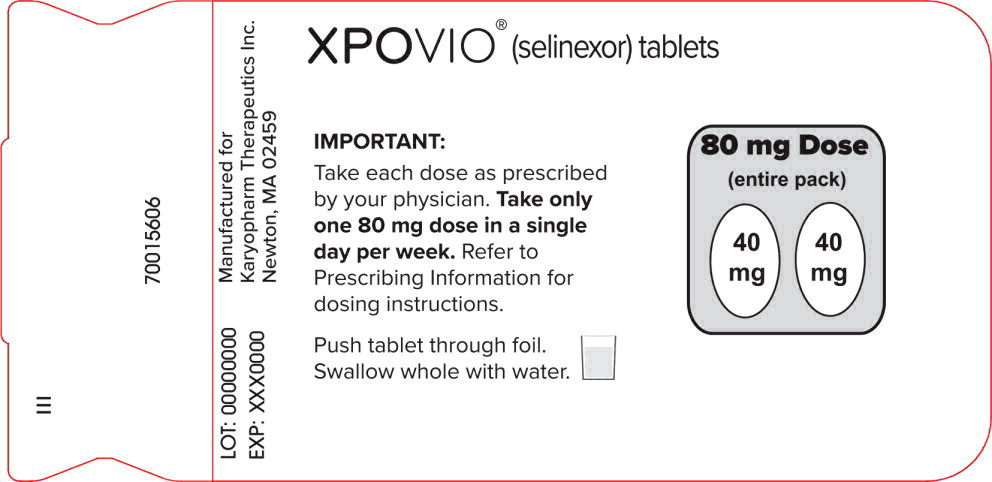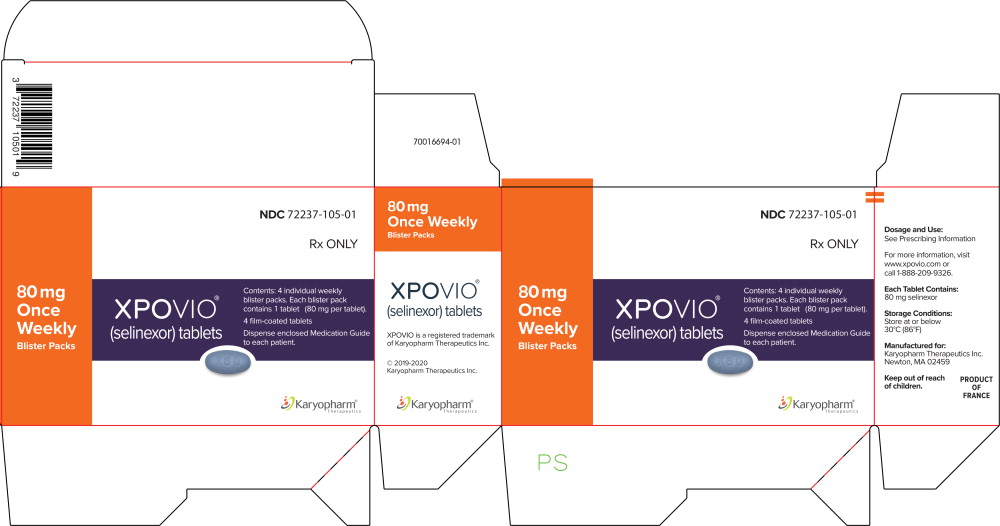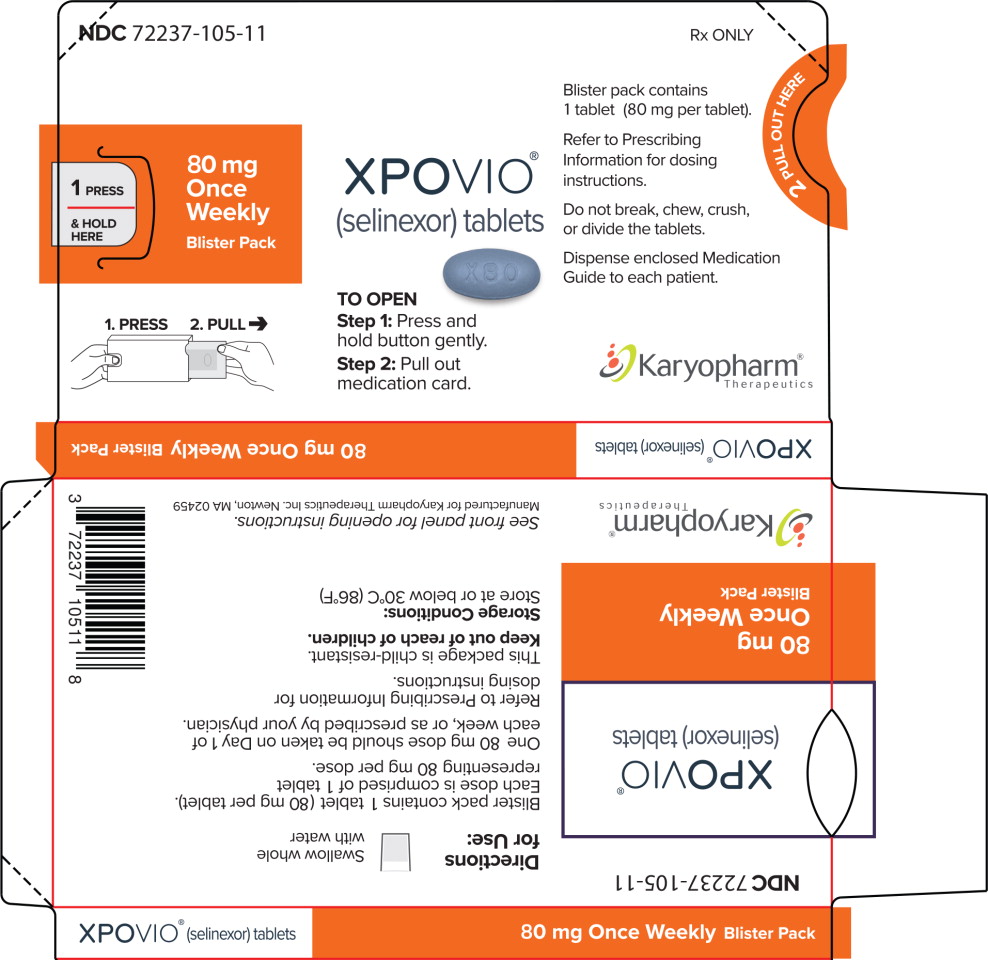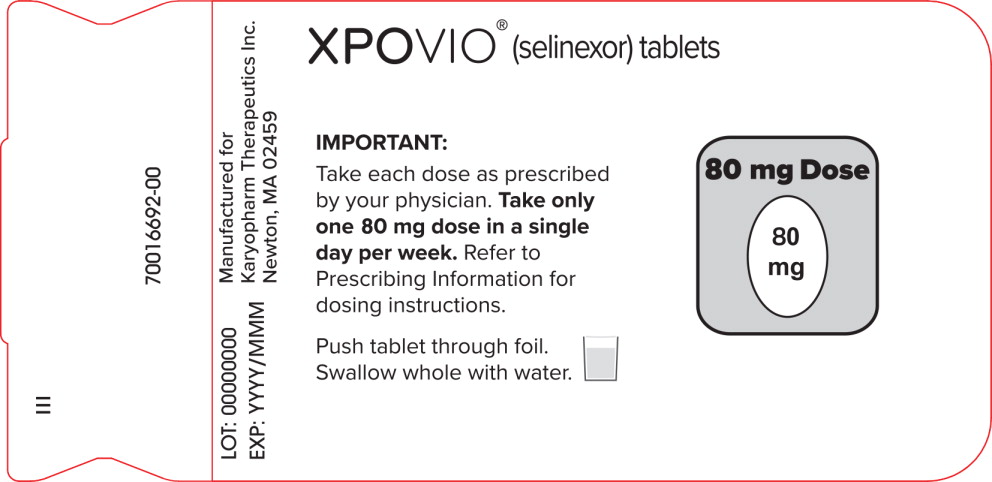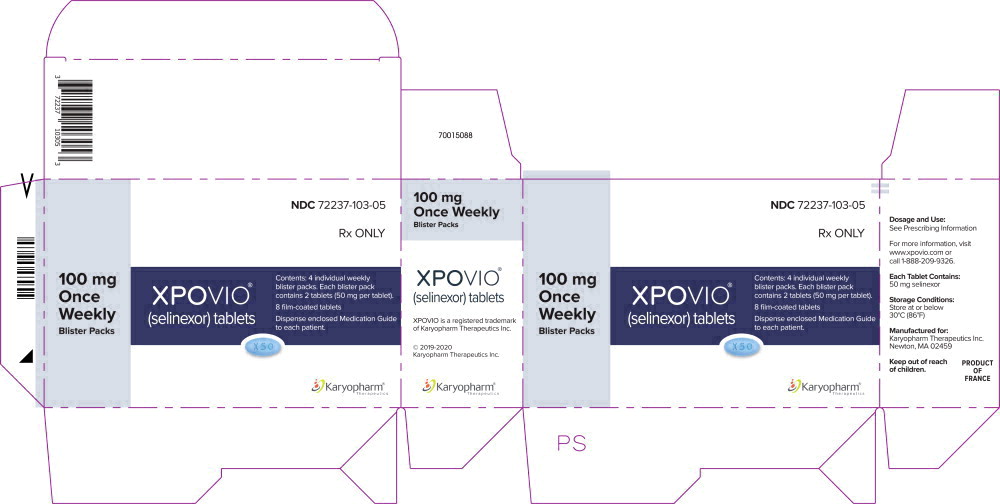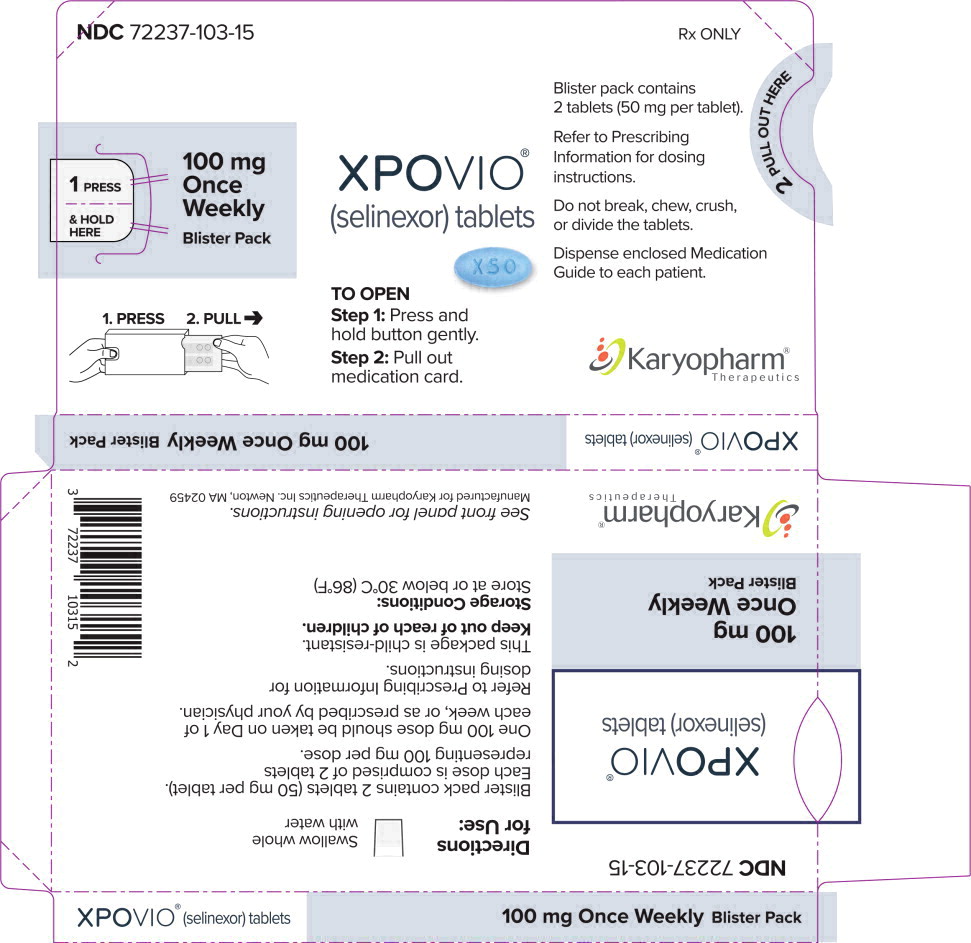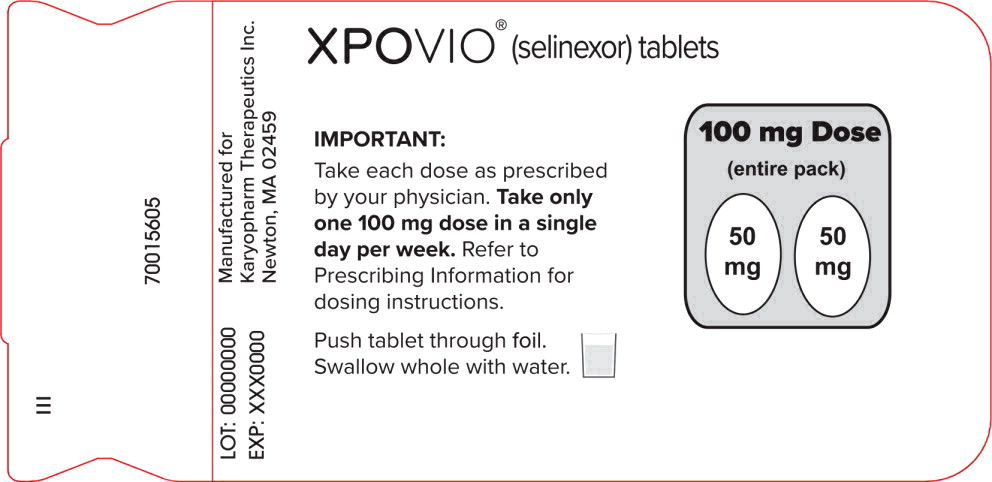 DRUG LABEL: XPOVIO
NDC: 72237-106 | Form: TABLET, FILM COATED
Manufacturer: Karyopharm Therapeutics Inc.
Category: prescription | Type: HUMAN PRESCRIPTION DRUG LABEL
Date: 20251029

ACTIVE INGREDIENTS: selinexor 10 mg/1 1
INACTIVE INGREDIENTS: Microcrystalline Cellulose 101; Microcrystalline Cellulose 102; Croscarmellose Sodium; Povidone K30; Sodium Lauryl Sulfate; Silicon Dioxide; Magnesium Stearate; TALC; POLYVINYL ALCOHOL, UNSPECIFIED; GLYCERYL MONOSTEARATE; POLYSORBATE 80; TITANIUM DIOXIDE; POLYETHYLENE GLYCOL 3350; FD&C BLUE NO. 2--ALUMINUM LAKE; FD&C BLUE NO. 1 ALUMINUM LAKE

HIGHLIGHTS OF PRESCRIBING INFORMATION

These highlights do not include all the information needed to use XPOVIO safely and effectively. See full prescribing information for XPOVIO.
XPOVIO® (selinexor) tablets, for oral use
Initial U.S. Approval: 2019

RECENT MAJOR CHANGES

Dosage and Administration, Starting Dosage and Dosage Modifications for Adverse Reactions in Patients with Severe Hepatic Impairment (2.6) 9/2025

1 INDICATIONS AND USAGE

XPOVIO is a nuclear export inhibitor indicated:

- In combination with bortezomib and dexamethasone for the treatment of adult patients with multiple myeloma who have received at least one prior therapy (1.1).
- In combination with dexamethasone for the treatment of adult patients with relapsed or refractory multiple myeloma who have received at least four prior therapies and whose disease is refractory to at least two proteasome inhibitors, at least two immunomodulatory agents, and an anti-CD38 monoclonal antibody (1.1).
- For the treatment of adult patients with relapsed or refractory diffuse large B-cell lymphoma (DLBCL), not otherwise specified, including DLBCL arising from follicular lymphoma, after at least 2 lines of systemic therapy. This indication is approved under accelerated approval based on response rate. Continued approval for this indication may be contingent upon verification and description of clinical benefit in confirmatory trial(s) (1.2).

2 DOSAGE AND ADMINISTRATION

- Multiple Myeloma in Combination with Bortezomib and Dexamethasone (XVd): Recommended dosage of XPOVIO is 100 mg taken orally once weekly in combination with bortezomib and dexamethasone (2.1).
- Multiple Myeloma in Combination with Dexamethasone (Xd): Recommended dosage of XPOVIO is 80 mg taken orally on Days 1 and 3 of each week in combination with dexamethasone (2.1).
- DLBCL: Recommended dosage of XPOVIO is 60 mg taken orally on Days 1 and 3 of each week (2.2).
- See Full Prescribing Information for dosage in patients with severe hepatic impairment (2.6, 8.6).

3 DOSAGE FORMS AND STRENGTHS

Tablets: 10mg, 20 mg, 40 mg, 50 mg, 60 mg, 80 mg(3).

4 CONTRAINDICATIONS

None (4).

5 WARNINGS AND PRECAUTIONS

- Thrombocytopenia: Monitor platelet counts throughout treatment. Manage with dose interruption and/or reduction and supportive care (2.5, 5.1).
- Neutropenia: Monitor neutrophil counts throughout treatment. Manage with dose interruption and/or reduction and granulocyte colony-stimulating factors (2.5, 5.2).
- Gastrointestinal Toxicity: Nausea, vomiting, diarrhea, anorexia, and weight loss may occur. Provide antiemetic prophylaxis. Manage with dose interruption and/or reduction, antiemetics, and supportive care (2.5, 5.3).
- Hyponatremia: Monitor serum sodium levels throughout treatment.
- Correct for concurrent hyperglycemia and high serum paraprotein levels. Manage with dose interruption, reduction, or discontinuation, and supportive care (2.5, 5.4).
- Serious Infection: Monitor for infection and treat promptly (5.2, 5.5).
- Neurological Toxicity: Advise patients to refrain from driving and engaging in hazardous occupations or activities until neurological toxicity resolves. Optimize hydration status and concomitant medications to avoid dizziness or mental status changes (5.6).
- Embryo-Fetal Toxicity: Can cause fetal harm. Advise females of reproductive potential and males with a female partner of reproductive potential, of the potential risk to a fetus and use of effective contraception (5.7, 8.1, 8.3).
- Cataract: Cataracts may develop or progress. Treatment of cataracts usually requires surgical removal of the cataract (5.8).

6 ADVERSE REACTIONS

- The most common adverse reactions (≥20%) in patients with multiple myeloma who receive XVd are fatigue, nausea, decreased appetite, diarrhea, peripheral neuropathy, upper respiratory tract infection, weight decreased, cataract, and vomiting. Grade 3-4 laboratory abnormalities (≥10%) are thrombocytopenia, lymphopenia, hypophosphatemia, anemia, hyponatremia, and neutropenia (6.1).
- The most common adverse reactions (≥20%) in patients with multiple myeloma who receive Xd are thrombocytopenia, fatigue, nausea, anemia, decreased appetite, weight decreased, diarrhea, vomiting, hyponatremia, neutropenia, leukopenia, constipation, dyspnea, and upper respiratory tract infection (6.1).
- The most common adverse reactions (incidence ≥20%) in patients with DLBCL, excluding laboratory abnormalities, are fatigue, nausea, diarrhea, decreased appetite, weight decreased, constipation, vomiting, and pyrexia. Grade 3-4 laboratory abnormalities (≥15%) are thrombocytopenia, lymphopenia, neutropenia, anemia, and hyponatremia (6.1).

To report SUSPECTED ADVERSE REACTIONS, contact Karyopharm Therapeutics Inc. at 1-888-209-9326 or FDA at 1-800-FDA-1088 or www.fda.gov/medwatch.

8 USE IN SPECIFIC POPULATIONS

Lactation: Advise not to breastfeed (8.2).

FULL PRESCRIBING INFORMATION

1 INDICATIONS AND USAGE

1.1 Multiple Myeloma

- XPOVIO in combination with bortezomib and dexamethasone is indicated for the treatment of adult patients with multiple myeloma who have received at least one prior therapy.
- XPOVIO in combination with dexamethasone is indicated for the treatment of adult patients with relapsed or refractory multiple myeloma who have received at least four prior therapies and whose disease is refractory to at least two proteasome inhibitors, at least two immunomodulatory agents, and an anti-CD38 monoclonal antibody.

1.2 Diffuse Large B-Cell Lymphoma

XPOVIO is indicated for the treatment of adult patients with relapsed or refractory diffuse large B-cell lymphoma (DLBCL), not otherwise specified, including DLBCL arising from follicular lymphoma, after at least 2 lines of systemic therapy.

This indication is approved under accelerated approval based on response rate [see Clinical Studies (14.2)]. Continued approval for this indication may be contingent upon verification and description of clinical benefit in a confirmatory trial(s).

2 DOSAGE AND ADMINISTRATION

2.1 Recommended Dosage for Multiple Myeloma

In Combination with Bortezomib and Dexamethasone (XVd)

The recommended dosage of XPOVIO is 100 mg taken orally once weekly on Day 1 of each week until disease progression or unacceptable toxicity in combination with:

- Bortezomib 1.3 mg/m^2 administered subcutaneously once weekly on Day 1 of each week for 4 weeks followed by 1 week off.
- Dexamethasone 20 mg taken orally twice weekly on Days 1 and 2 of each week.

Refer to Clinical Studies (14.1) and the prescribing information of bortezomib and dexamethasone for additional dosing information.

In Combination with Dexamethasone (Xd)

The recommended dosage of XPOVIO is 80 mg taken orally on Days 1 and 3 of each week until disease progression or unacceptable toxicity in combination with dexamethasone 20 mg taken orally with each dose of XPOVIO on Days 1 and 3 of each week.

For additional information regarding the administration of dexamethasone, refer to its prescribing information.

2.2 Recommended Dosage for Diffuse Large B-Cell Lymphoma

The recommended dosage of XPOVIO is 60 mg taken orally on Days 1 and 3 of each week until disease progression or unacceptable toxicity.

2.3 Recommended Monitoring for Safety

Monitor complete blood count (CBC) with differential, standard blood chemistries, body weight, nutritional status, and volume status at baseline and during treatment as clinically indicated. Monitor more frequently during the first three months of treatment [see Warning and Precautions (5.1, 5.2, 5.3, and 5.4)]. Assess the need for dosage modifications of XPOVIO for adverse reactions [see Dosage and Administration (2.5)].

2.4 Recommended Concomitant Treatments

Advise patients to maintain adequate fluid and caloric intake throughout treatment. Consider intravenous hydration for patients at risk of dehydration [see Warnings and Precautions (5.3, 5.4)].

Provide prophylactic antiemetics. Administer a 5-HT3 receptor antagonist and other anti-nausea agents prior to and during treatment with XPOVIO [see Warnings and Precautions (5.3)].

2.5 Dosage Modifications for Adverse Reactions

Recommended XPOVIO dosage reduction steps are presented in Table 1.

Table 1: XPOVIO Dosage Reduction Steps for Adverse Reactions
Recommended Starting Dosage | Multiple Myeloma In Combination with Bortezomib and Dexamethasone (XVd) | Multiple Myeloma In Combination with Dexamethasone (Xd) | Diffuse Large B-Cell Lymphoma
Recommended Starting Dosage | 100 mg once weekly | 80 mg Days 1 and 3 of each week (160 mg total per week) | 60 mg Days 1 and 3 of each week (120 mg total per week)
First Reduction | 80 mg once weekly | 100 mg once weekly | 40 mg Days 1 and 3 of each week (80 mg total per week)
Second Reduction | 60 mg once weekly | 80 mg once weekly | 60 mg once weekly
Third Reduction | 40 mg once weekly | 60 mg once weekly | 40 mg once weekly
Fourth Reduction | Permanently discontinue | Permanently discontinue | Permanently discontinue

Recommended dosage modifications for hematologic adverse reactions in patients with multiple myeloma and DLBCL are presented in Table 2 and Table 3, respectively. Recommended dosage modifications for nonhematologic adverse reactions are presented in Table 4.

Table 2: XPOVIO Dosage Modification Guidelines for Hematologic Adverse Reactions in Patients with Multiple Myeloma
Adverse Reaction | Occurrence | Action
Thrombocytopenia [see Warning and Precautions (5.1)]
Platelet count 25,000 to less than 75,000/mcL | Any | - Reduce XPOVIO by 1 dose level (see Table 1).
Platelet count 25,000 to less than 75,000/mcL with concurrent bleeding | Any | - Interrupt XPOVIO. - Restart XPOVIO at 1 dose level lower (see Table 1) after bleeding has resolved. - Administer platelet transfusions per clinical guidelines.
Platelet count less than 25,000/mcL | Any | - Interrupt XPOVIO. - Monitor until platelet count returns to at least 50,000/mcL. - Restart XPOVIO at 1 dose level lower (see Table 1).
Adverse Reaction | Occurrence | Action
Neutropenia [see Warning and Precautions (5.2)]
Absolute neutrophil count of 0.5 to 1 x 10^9/L without fever | Any | - Reduce XPOVIO by 1 dose level (see Table 1).
Absolute neutrophil count less than 0.5 x 10^9/L OR febrile neutropenia | Any | - Interrupt XPOVIO. - Monitor until neutrophil counts return to 1 x 10^9/L or higher. - Restart XPOVIO at 1 dose level lower (see Table 1).
Anemia
Hemoglobin less than 8 g/dL | Any | - Reduce XPOVIO by 1 dose level (see Table 1). - Administer blood transfusions per clinical guidelines.
Life-threatening consequences | Any | - Interrupt XPOVIO. - Monitor hemoglobin until levels return to 8 g/dL or higher. - Restart XPOVIO at 1 dose level lower (see Table 1). - Administer blood transfusions per clinical guidelines.

Table 3: XPOVIO Dosage Modification Guidelines for Hematologic Adverse Reactions in Patients with Diffuse Large B-Cell Lymphoma
Adverse Reaction | Occurrence | Action
Thrombocytopenia [see Warning and Precautions (5.1)]
Platelet count 50,000 to less than 75,000/mcL | Any | - Interrupt one dose of XPOVIO. - Restart XPOVIO at the same dose level.
Platelet count 25,000 to less than 50,000/mcL without bleeding | 1st | - Interrupt XPOVIO. - Monitor until platelet count returns to at least 50,000/mcL. - Reduce XPOVIO by 1 dose level (see Table 1).
Platelet count 25,000 to less than 50,000/mcL with concurrent bleeding | Any | - Interrupt XPOVIO. - Monitor until platelet count returns to at least 50,000/mcL. - Restart XPOVIO at 1 dose level lower (see Table 1), after bleeding has resolved. - Administer platelet transfusions per clinical guidelines.
Platelet count less than 25,000/mcL | Any | - Interrupt XPOVIO. - Monitor until platelet count returns to at least 50,000/mcL. - Restart XPOVIO at 1 dose level lower (see Table 1). - Administer platelet transfusions per clinical guidelines.
Neutropenia [see Warning and Precautions (5.2)]
Absolute neutrophil count of 0.5 to less than 1 x 10^9/L without fever | 1st occurrence | - Interrupt XPOVIO. - Monitor until neutrophil counts return to 1 x 10^9/L or higher. - Restart XPOVIO at the same dose level.
Absolute neutrophil count of 0.5 to less than 1 x 10^9/L without fever | Recurrence | - Interrupt XPOVIO. - Monitor until neutrophil counts return to 1 x 10^9/L or higher. - Administer growth factors per clinical guidelines. - Restart XPOVIO at 1 dose level lower (see Table 1).
Absolute neutrophil count less than 0.5 x 10^9/L OR Febrile neutropenia | Any | - Interrupt XPOVIO. - Monitor until neutrophil counts return to 1 x 10^9/L or higher. - Administer growth factors per clinical guidelines. - Restart XPOVIO at 1 dose level lower (see Table 1).
Anemia
Hemoglobin less than 8 g/dL | Any | - Reduce XPOVIO by 1 dose level (see Table 1). - Administer blood transfusions per clinical guidelines.
Life-threatening consequences | Any | - Interrupt XPOVIO. - Monitor hemoglobin until levels return to 8 g/dL or higher. - Restart XPOVIO at 1 dose level lower (see Table 1). - Administer blood transfusions per clinical guidelines.

Table 4: XPOVIO Dosage Modification Guidelines for Non-Hematologic Adverse Reactions
Adverse Reaction | Occurrence | Action
Nausea and Vomiting [see Warning and Precautions (5.3)]
Grade 1 or 2 nausea (oral intake decreased without significant weight loss, dehydration or malnutrition) OR Grade 1 or 2 vomiting (5 or fewer episodes per day) | Any | - Maintain XPOVIO and initiate additional anti-nausea medications.
Grade 3 nausea (inadequate oral caloric or fluid intake) OR Grade 3 or higher vomiting (6 or more episodes per day) | Any | - Interrupt XPOVIO. - Monitor until nausea or vomiting has resolved to Grade 2 or lower or baseline. - Initiate additional anti-nausea medications. - Restart XPOVIO at 1 dose level lower (see Table 1).
Diarrhea [see Warning and Precautions (5.3)]
Grade 2 (increase of 4 to 6 stools per day over baseline) | 1st | - Maintain XPOVIO and institute supportive care.
Grade 2 (increase of 4 to 6 stools per day over baseline) | 2nd and subsequent | - Reduce XPOVIO by 1 dose level (see Table 1). - Institute supportive care.
Grade 3 or higher (increase of 7 stools or more per day over baseline; hospitalization indicated) | Any | - Interrupt XPOVIO and institute supportive care. - Monitor until diarrhea resolves to Grade 2 or lower. - Restart XPOVIO at 1 dose level lower (see Table 1).
Weight Loss and Anorexia [see Warning and Precautions (5.3)]
Weight loss of 10% to less than 20% OR Anorexia associated with significant weight loss or malnutrition | Any | - Interrupt XPOVIO and institute supportive care. - Monitor until weight returns to more than 90% of baseline weight. - Restart XPOVIO at 1 dose level lower (see Table 1).
Hyponatremia [see Warning and Precautions (5.4)]
Sodium level 130 mmol/L or less | Any | - Interrupt XPOVIO, evaluate, and provide supportive care. - Monitor until sodium levels return to greater than 130 mmol/L. - Restart XPOVIO at 1 dose level lower (see Table 1).
Fatigue
Grade 2 lasting greater than 7 days OR Grade 3 | Any | - Interrupt XPOVIO. - Monitor until fatigue resolves to Grade 1 or baseline. - Restart XPOVIO at 1 dose level lower (see Table 1).
Ocular Toxicity [see Warning and Precautions (5.8)]
Grade 2, excluding cataract | Any | - Perform ophthalmologic evaluation. - Interrupt XPOVIO and provide supportive care. - Monitor until ocular symptoms resolve to Grade 1 or baseline. - Restart XPOVIO at 1 dose level lower (see Table 1).
Grade ≥3, excluding cataract | Any | - Permanently discontinue XPOVIO. - Perform ophthalmologic evaluation.
Other Non-Hematologic Adverse Reactions [see Warning and Precautions (5.6)]
Grade 3 or 4 | Any | - Interrupt XPOVIO. - Monitor until resolved to Grade 2 or lower; restart XPOVIO at 1 dose level lower (see Table 1).

2.6 Starting Dosage and Dosage Modifications for Adverse Reactions in Patients with Severe Hepatic Impairment

For patients with severe hepatic impairment, defined by NCI-ODWG (National Cancer Institute Organ Dysfunction Working Group) criteria as total bilirubin >3x upper limit of normal with any level of AST, use the starting dosage of XPOVIO as shown in Table 5 [see Use in Specific Populations (8.6) and Clinical Pharmacology (12.3)]. See Table 6 for dosage modifications for adverse reactions in patients with severe hepatic impairment.

Table 5: XPOVIO Starting Dosage in Patients with Severe Hepatic Impairment
Total Bilirubin Levels | XPOVIO Dosage
Total Bilirubin Levels | Multiple Myeloma in Combination with Bortezomib and Dexamethasone (XVd) | Multiple Myeloma in Combination with Dexamethasone (Xd) | Diffuse Large B Cell Lymphoma
>3x ULN (and any AST) | 80 mg once weekly | 100 mg once weekly | 40 mg Days 1 and 3 of each week (80 mg total per week)
AST = aspartate aminotransferase; ULN = upper limit of normal

Table 6: XPOVIO Dosage Modifications for Adverse Reactions for Patients with Severe Hepatic Impairment
 | Multiple Myeloma In Combination with Bortezomib and Dexamethasone (XVd) | Multiple Myeloma In Combination with Dexamethasone (Xd) | Diffuse Large B-Cell Lymphoma
Recommended Starting Dosage | 80 mg once weekly | 100 mg once weekly | 40 mg Days 1 and 3 of each week (80 mg total per week)
First Reduction | 60 mg once weekly | 80 mg once weekly | 60 mg once weekly
Second Reduction | 40 mg once weekly | 60 mg once weekly | 40 mg once weekly
Third Reduction | Permanently discontinue | Permanently discontinue | Permanently discontinue

2.7 Administration

Each XPOVIO dose should be taken at approximately the same time of day and each tablet should be swallowed whole with water. Do not break, chew, crush, or divide the tablets.

If a dose of XPOVIO is missed or delayed, instruct patients to take their next dose at the next regularly scheduled time.

If a patient vomits a dose of XPOVIO, the patient should not repeat the dose and the patient should take the next dose on the next regularly scheduled day.

3 DOSAGE FORMS AND STRENGTHS

Tablets:

10 mg, blue, round, bi-convex, film-coated tablets with “X10” debossed on one side and nothing on the other side.

20 mg, blue, round, bi-convex, film-coated tablets with “K20” debossed on one side and nothing on the other side.

40 mg tablets, blue, oval, film-coated, debossed on both sides with “X40”.

50 mg tablets, blue, oval, film-coated, debossed on both sides with “X50”.

60 mg tablets, blue, oval, film-coated, debossed on both sides with “X60”.

80 mg tablets, blue, oval, film-coated, debossed on both sides with “X80”.

4 CONTRAINDICATIONS

None.

5 WARNINGS AND PRECAUTIONS

5.1 Thrombocytopenia

XPOVIO can cause life-threatening thrombocytopenia, potentially leading to hemorrhage. Thrombocytopenia is the leading cause of dosage modifications [see Adverse Reactions (6.1)].

In patients with multiple myeloma who received XPOVIO 100 mg once weekly (BOSTON, n=195), thrombocytopenia was reported in 92% of patients and severe (Grade 3-4) thrombocytopenia was reported in 43% of patients. The median time to first onset was 22 days for any grade thrombocytopenia and 43 days for Grade 3 or 4 thrombocytopenia. Bleeding occurred in 16% of patients with thrombocytopenia, clinically significant bleeding (Grade ≥3 bleeding) occurred in 4% of patients with thrombocytopenia, and fatal hemorrhage occurred in 2% of patients with thrombocytopenia. Permanent discontinuations of XPOVIO due to thrombocytopenia occurred in 2% of patients.

In patients with multiple myeloma who received XPOVIO 80 mg twice weekly (STORM, n=202), thrombocytopenia was reported as an adverse reaction in 74% of patients and severe (Grade 3-4) thrombocytopenia was reported in 61% of patients. The median time to onset of the first event was 22 days. Bleeding occurred in 23% of patients with thrombocytopenia, clinically significant bleeding occurred in 5% of patients with thrombocytopenia, and fatal hemorrhage occurred in <1% of patients.

In patients with DLBCL who received XPOVIO 60 mg twice weekly (SADAL, n=134), thrombocytopenia developed or worsened in 86% of patients, including Grade 3-4 thrombocytopenia in 49% of patients (Grade 4, 18%). The median time to first onset was 28 days for any grade thrombocytopenia and 33 days for Grade 3 or 4 thrombocytopenia.

Monitor platelet counts at baseline and throughout treatment. Monitor more frequently during the first three months of treatment. Institute platelet transfusion and/or other treatments as clinically indicated. Monitor patients for signs and symptoms of bleeding and evaluate promptly. Interrupt, reduce dose, or permanently discontinue based on severity of adverse reaction [see Dosage and Administration (2.5)].

5.2 Neutropenia

XPOVIO can cause life-threatening neutropenia, potentially increasing the risk of infection [see Adverse Reactions (6.1)].

In patients with multiple myeloma who received XPOVIO 100 mg once weekly (BOSTON, n=195), neutropenia was reported in 48% of patients and severe neutropenia (Grade 3-4) was reported in 12% of patients. The median time to onset of the first event was 23 days for any grade neutropenia and 40 days for Grade 3-4 neutropenia. Febrile neutropenia was reported in <1% of patients.

In patients with multiple myeloma who received XPOVIO 80 mg twice weekly (STORM, n=202), neutropenia was reported as an adverse reaction in 34% of patients and severe (Grade 3-4) neutropenia was reported in 21% of patients. The median time to onset of the first event was 25 days. Febrile neutropenia was reported in 3% of patients.

In patients with DLBCL (SADAL, n=134), Grade 3 neutropenia developed in 21% of patients and Grade 4 neutropenia developed in 9% of patients. The median time to first onset of Grade 3 or 4 neutropenia was 32 days. Febrile neutropenia was reported in 3% of patients.

Obtain white blood cell counts with differential at baseline and throughout treatment. Monitor more frequently during the first three months of treatment. Monitor patients for signs and symptoms of concomitant infection and evaluate promptly. Consider supportive measures, including antimicrobials and growth factors (e.g., G-CSF). Interrupt, reduce dose or permanently discontinue based on severity of adverse reaction [see Dosage and Administration (2.5)].

5.3 Gastrointestinal Toxicity

XPOVIO can cause severe gastrointestinal toxicities [see Adverse Reactions (6.1)]. In patients with DLBCL (n=134), gastrointestinal toxicity occurred in 80% of patients with Grade 3 or 4 in 13%.

Nausea/Vomiting

In patients with multiple myeloma who received XPOVIO once weekly (BOSTON, n=195) with use of antiemetic prophylaxis (88% of patients), nausea was reported in 50% of patients and Grade 3 nausea was reported in 8% of patients. The median time to onset of the first event was 6 days. Vomiting was reported in 21% of patients and Grade 3 vomiting was reported in 4.1% of patients. The median time to onset of the first event was 8 days. Permanent discontinuation due to nausea occurred in 3.1% of patients and due to vomiting occurred in 2.1% of patients.

In patients with multiple myeloma receiving XPOVIO 80 mg twice weekly (STORM, n=202) with use of antiemetic prophylaxis, nausea was reported as an adverse reaction in 72% of patients and Grade 3 nausea occurred in 9%. The median time to first onset of nausea was 3 days. Vomiting was reported in 41% of patients and Grade 3 vomiting occurred in 4% of patients. The median time to first onset of vomiting was 5 days.

In patients with DLBCL (SADAL, n=134) with use of antiemetic prophylaxis, nausea occurred in 57% of patients and Grade 3 nausea occurred in 6% of patients. Vomiting occurred in 28% of patients and Grade 3 vomiting occurred in 1.5% of patients. The median time to first onset was 3 days for nausea and 7 days for vomiting.

Provide prophylactic antiemetics. Administer 5-HT3 receptor antagonists and other anti-nausea agents prior to and during treatment with XPOVIO. Interrupt, reduce dose or permanently discontinue based on severity of adverse reaction [see Dosage and Administration (2.5)]. Administer intravenous fluids to prevent dehydration and replace electrolytes as clinically indicated.

Diarrhea

In patients with multiple myeloma who received XPOVIO once weekly (BOSTON, n=195), diarrhea was reported in 32% of patients and Grade 3 diarrhea was reported in 6% of patients. The median time to onset of the first event was 50 days. Permanent discontinuation due to diarrhea occurred in 1% of patients.

In patients with multiple myeloma who received XPOVIO 80 mg twice weekly (STORM, n=202), diarrhea was reported as an adverse reaction in 44% of patients and Grade 3 diarrhea occurred in 6% of patients. The median time to onset of diarrhea was 15 days.

In patients with DLBCL (SADAL, n=134), diarrhea occurred in 37% of patients and Grade 3 diarrhea occurred in 3% of patients treated with XPOVIO. The median time to onset of the first event was 12 days.

Interrupt, reduce dose or permanently discontinue based on severity of adverse reaction [see Dosage and Administration (2.5)]. Provide standard anti-diarrheal agents, administer intravenous fluids to prevent dehydration and replace electrolytes as clinically indicated.

Anorexia/Weight Loss

In patients with multiple myeloma who received XPOVIO 100 mg once weekly (BOSTON, n=195), anorexia was reported in 35% of patients and Grade 3 anorexia was reported in 3.6% of patients. The median time to onset of the first event was 35 days. Permanent discontinuations due to anorexia occurred in 2.1% of patients. Weight loss was reported in 26% of patients and Grade 3 weight loss was reported in 2.1% of patients. The median time to onset of the first event was 58 days. Permanent discontinuation due to weight loss occurred in 1% of patients.

In patients with multiple myeloma who received XPOVIO 80 mg twice weekly (STORM n=202), anorexia was reported as an adverse reaction in 53% of patients and Grade 3 anorexia occurred in 5% of patients. The median time to onset of anorexia was 8 days. Weight loss was reported as an adverse reaction in 47% of patients and Grade 3 weight loss occurred in 1% of patients treated with XPOVIO. The median time to onset of weight loss was 15 days.

In patients with DLBCL (SADAL, n=134), anorexia was reported as an adverse reaction in 37% of patients and Grade 3 anorexia occurred in 3.7% of patients treated with XPOVIO. Weight loss (Grade 1-2) was reported as an adverse reaction in 30% of patients.

Monitor weight, nutritional status, and volume status at baseline and throughout treatment. Monitor more frequently during the first three months of treatment. Interrupt, reduce dose or permanently discontinue based on severity of adverse reaction [see Dosage and Administration (2.5)]. Provide nutritional support, fluids, and electrolyte repletion as clinically indicated.

5.4 Hyponatremia

XPOVIO can cause severe or life-threatening hyponatremia [see Adverse Reactions (6.1)].

In patients with multiple myeloma who received XPOVIO 100 mg once weekly (BOSTON, n=195), hyponatremia was reported in 58% of patients and Grade 3-4 hyponatremia was reported in 14% of patients. The median time to first onset was 21 days for any grade hyponatremia and the median time to first onset for Grade 3 or 4 hyponatremia was 22 days.

In patients with multiple myeloma who received XPOVIO 80 mg twice weekly (STORM, n=202), hyponatremia was reported as an adverse reaction in 39% of patients and Grade 3 or 4 hyponatremia was reported in 22% of patients. The median time to onset of the first event was 8 days.

In patients with DLBCL (SADAL, n=134), hyponatremia developed in 62% of patients and Grade 3 hyponatremia developed in 16% of patients treated with XPOVIO. In approximately 63% of cases, hyponatremia occurred in the context of gastrointestinal toxicity such as nausea, vomiting, diarrhea, dehydration, and anorexia.

Monitor sodium level at baseline and throughout treatment. Monitor more frequently during the first two months of treatment. Correct sodium levels for concurrent hyperglycemia (serum glucose >150 mg/dL) and high serum paraprotein levels. Assess hydration status and manage hyponatremia per clinical guidelines, including intravenous saline and/or salt tablets as appropriate and dietary review. Interrupt, reduce dose or permanently discontinue based on severity of the adverse reaction [see Dosage and Administration (2.5)].

5.5 Serious Infection

XPOVIO can cause serious and fatal infections. Most of these infections were not associated with Grade 3 or higher neutropenia [see Adverse Reactions (6.1)].

In patients with multiple myeloma who received XPOVIO 100 mg once weekly (BOSTON, n=195), 69% of patients experienced any grade of infection. Grade ≥3 infections were reported in 32% of patients, and deaths from infections occurred in 3.1% of patients. The most frequently reported Grade ≥3 infection was pneumonia in 14% of patients, followed by sepsis in 4.1% and upper respiratory tract infection in 3.6% of patients.

In patients with multiple myeloma who received XPOVIO 80 mg twice weekly (STORM, n=202), 52% of patients experienced any grade of infection. Grade ≥3 infections were reported in 25% of patients, and deaths from infections occurred in 4% of patients within 30 days of last treatment. Upper respiratory tract infection of any grade occurred in 21%, pneumonia in 13%, and sepsis in 6% of patients. The most frequently reported Grade ≥3 infections were pneumonia in 9% of patients, followed by sepsis in 6%. The median time to onset was 54 days for pneumonia and 42 days for sepsis.

In patients with DLBCL (SADAL, n=134), 25% of patients experienced Grade 3 or higher infection and 21% had an infection-related serious adverse reaction; 49% developed an infection of any grade, most frequently involving the upper or lower respiratory tract. The most frequently reported Grade ≥3 infections were lower respiratory tract infections in 9% of patients (including pneumonia in 6%), followed by sepsis (6%). The median time to onset of Grade ≥3 infection was 42 days.

Atypical infections reported after XPOVIO include, but are not limited to, fungal pneumonia and herpes virus infection.

Monitor for signs and symptoms of infection, evaluate and treat promptly.

5.6 Neurological Toxicity

XPOVIO can cause life-threatening neurological toxicities [see Adverse Reactions (6.1)].

In patients with multiple myeloma who received XPOVIO 100 mg once weekly (BOSTON, n=195), neurological adverse reactions (excluding peripheral neuropathy) including dizziness, syncope, depressed level of consciousness, vertigo, amnesia, and mental status changes (including delirium and confusional state) occurred in 26% of patients and severe events (Grade 3-4) occurred in 3.6% of patients. The median time to the first event was 29 days. Permanent discontinuation due to neurological adverse reactions occurred in 2.1% of patients.

In patients with multiple myeloma who received XPOVIO 80 mg twice weekly (STORM, n=202), neurological adverse reactions, including dizziness, syncope, depressed level of consciousness, and mental status changes (including delirium and confusional state) occurred in 30% of patients and severe events (Grade 3-4) occurred in 9% of patients. The median time to the first event was 15 days.

In patients with DLBCL (SADAL, n=134), neurological adverse reactions occurred in 25% of patients and severe events (Grade 3-4) occurred in 6% of patients treated with XPOVIO. The most frequent manifestations were dizziness (16%) and mental status changes (11%), including confusion, cognitive disorders, somnolence, hallucination, delirium, and depressed level of consciousness. Syncope occurred in 2.2% of patients. The median time to the first event was 28 days. Among patients with such neurological adverse reactions, 68% recovered with a median time to recovery of 14 days.

Coadministration of XPOVIO with other products that cause dizziness or mental status changes may increase the risk of neurological toxicity.

Advise patients to refrain from driving and engaging in hazardous occupations or activities, such as operating heavy or potentially dangerous machinery, until the neurological toxicity fully resolves. Optimize hydration status, hemoglobin level, and concomitant medications to avoid exacerbating dizziness or mental status changes. Institute fall precautions as appropriate.

5.7 Embryo-Fetal Toxicity

Based on data from animal studies and its mechanism of action, XPOVIO can cause fetal harm when administered to a pregnant woman. Selinexor administration to pregnant animals during organogenesis resulted in structural abnormalities and alterations to growth at exposures below those occurring clinically at the recommended dose.

Advise pregnant women of the potential risk to a fetus. Advise females of reproductive potential and males with a female partner of reproductive potential to use effective contraception during treatment with XPOVIO and for 1 week after the last dose [see Use in Specific Populations (8.1, 8.3)].

5.8 Cataract

New onset or exacerbation of cataract has occurred during treatment with XPOVIO [see Adverse Reactions (6.1)]. In patients with multiple myeloma who received XPOVIO 100 mg once weekly (BOSTON, n=195), the incidence of new onset or worsening cataracts requiring clinical intervention was reported in 22% of patients. The median time to new onset of cataract was 228 days and was 237 days for worsening of cataract in patients presenting with cataract at start of XPOVIO therapy. Treatment of cataracts usually requires surgical removal of the cataract.

6 ADVERSE REACTIONS

The following clinically significant adverse reactions are described in detail in other labeling sections:

- Thrombocytopenia [see Warnings and Precautions (5.1)].
- Neutropenia [see Warnings and Precautions (5.2)].
- Gastrointestinal Toxicity [see Warnings and Precautions (5.3)].
- Hyponatremia [see Warnings and Precautions (5.4)].
- Serious Infection [see Warnings and Precautions (5.5)].
- Neurological Toxicity [see Warnings and Precautions (5.6)].
- Cataract [see Warnings and Precautions (5.8)].

6.1 Clinical Trials Experience

Because clinical trials are conducted under widely varying conditions, adverse reaction rates observed in the clinical trials of a drug cannot be directly compared to rates in the clinical trials of another drug and may not reflect the rates observed in practice.

Multiple Myeloma

XPOVIO in Combination with Bortezomib and Dexamethasone (XVd)

The safety of XPOVIO in combination with bortezomib and dexamethasone was evaluated in BOSTON [see Clinical Studies (14.1)]. Patients were randomized to receive XPOVIO 100 mg orally once weekly in combination with bortezomib and dexamethasone (XVd) (n=195) or bortezomib and dexamethasone (Vd) (n=204). Among patients who received XPOVIO, the median duration of XPOVIO treatment was 29 weeks (range: 1 to 120 weeks) and the median dose was 80 mg (range: 30 to 137 mg) per week.

Serious adverse reactions occurred in 52% of patients who received XPOVIO in combination with bortezomib and dexamethasone. Serious adverse reactions in >3% of patients included pneumonia (14%), sepsis, diarrhea and vomiting (4% each). Fatal adverse reactions occurred in 6% of patients within 30 days of last treatment, including pneumonia (n=3) and sepsis (n=3).

Grade ≥2 peripheral neuropathy, a pre-specified key secondary endpoint, was lower in the XVd arm (21%) compared to the Vd arm (34%); odds ratio 0.50 [95% CI: 0.32, 0.79]. The median treatment duration was 30 weeks (range: 1-120 weeks) in patients who received once weekly XVd as compared to 32 weeks (range: 1-122 weeks) in patients who received twice weekly Vd.

Permanent discontinuation of XPOVIO due to an adverse reaction occurred in 19% of patients. Adverse reactions which resulted in permanent discontinuation of XPOVIO in >2% of patients included fatigue (3.6%), nausea (3.1%), thrombocytopenia, decreased appetite, peripheral neuropathy, and vomiting (2.1% each).

Dosage interruptions of XPOVIO due to an adverse reaction occurred in 83% of patients. Adverse reactions which required dosage interruption in >5% of patients included thrombocytopenia (33%), fatigue (13%), asthenia (12%), pneumonia (11%), upper respiratory tract infection (10%), decreased appetite (9%), neutropenia (8%), pyrexia (8%), nausea (7%), bronchitis (7%), diarrhea (6%), weight decreased (6%), and anemia (5%).

Dose reductions of XPOVIO due to an adverse reaction occurred in 64% of patients. Adverse reactions which required dose reductions in >5% of patients included thrombocytopenia (31%), decreased appetite (8%), nausea, fatigue, weight decreased (7% each), and asthenia (6%).

The most common adverse reactions (≥20% with a difference between arms of >5% compared to Vd) were fatigue, nausea, decreased appetite, diarrhea, peripheral neuropathy, upper respiratory tract infection, weight decreased, cataract, and vomiting. Grade 3-4 laboratory abnormalities (≥10%) were thrombocytopenia, lymphopenia, hypophosphatemia, anemia, hyponatremia, and neutropenia.

Table 7 summarizes the adverse reactions in BOSTON.

Table 7: Adverse Reactions (≥10%) in Patients with Multiple Myeloma Who Received XPOVIO in Combination with Bortezomib and Dexamethasone (XVd) with a Difference Between Arms of >5% Compared to Vd in BOSTON
Adverse Reaction | Weekly XVd (n=195) |  | Twice Weekly Vd (n=204)
Adverse Reaction | All Grades (%) | Grade 3 or 4 (%) | All Grades (%) | Grade 3 or 4 (%)
Gastrointestinal Nausea | 50 | 8 | 10 | 0
Diarrhea | 32 | 6 | 25 | <1
Vomiting | 21 | 4.1 | 4.4 | 0
General Conditions Fatiguea | 59 | 21 | 28 | 5
Pyrexia | 15 | 1.5 | 11 | 1
Metabolism and Nutrition Decreased appetite | 35 | 3.6 | 5 | 0
Weight decreased | 26 | 2.1 | 12 | 1
Nervous System Peripheral neuropathyb | 32 | 4.6 | 47 | 9
Dizziness | 12 | <1 | 3.9 | 0
Infections Upper respiratory tract infectionc | 29 | 3.6 | 22 | 1.5
Eye Disorders Cataract | 22 | 9 | 6 | 1.5
Vision blurredd | 13 | <1 | 6 | 0
Key: X=XPOVIO, Vd=bortezomib-dexamethasone
a. Fatigue includes fatigue and asthenia.
b. Peripheral neuropathy includes neuropathy peripheral, peripheral sensory neuropathy, polyneuropathy, peripheral sensorimotor neuropathy, toxic neuropathy, and peripheral motor neuropathy.
c. Upper respiratory tract infection includes upper respiratory infection, nasopharyngitis, pharyngitis, respiratory syncytial virus infection, respiratory tract infection, rhinitis, and viral upper respiratory tract infection.
d. Vision blurred includes blurred vision, visual acuity reduced, and visual impairment.

Clinically relevant adverse reactions in <10% of patients who received XPOVIO in combination with bortezomib and dexamethasone included:

- Neurologic disorders: mental status changes (9%) and syncope (3.6%)

Table 8 summarizes selected laboratory abnormalities in BOSTON.

Table 8: Select Laboratory Abnormalities (≥15%) That Worsened from Baseline in Patients with Multiple Myeloma Who Received XPOVIO in Combination with Bortezomib and Dexamethasone (XVd) in BOSTON
Laboratory Abnormality | Weekly XVd |  | Twice Weekly Vd
Laboratory Abnormality | All Grades (%) | Grade 3 or 4 (%) | All Grades (%) | Grade 3 or 4 (%)
Hematologic Platelet count decrease | 92 | 43 | 51 | 19
Lymphocyte count decrease | 77 | 38 | 70 | 27
Hemoglobin decrease | 71 | 17 | 51a | 12
Neutrophil count decrease | 48 | 12 | 19 | 7
Chemistry Glucose increase | 62 | 3.8 | 47 | 4.1
Phosphate decrease | 61 | 23 | 42 | 11
Sodium decrease | 58 | 14 | 25 | 3
Calcium decrease | 55 | 2.1 | 47 | 1
Blood urea nitrogen increase | 41 | 5 | 40 | 5
Creatinine increase | 28 | 3.6 | 24 | 1.5
Potassium decrease | 27 | 6 | 22 | 3.5
Magnesium decrease | 27 | <1 | 23 | 1.5
Potassium increase | 18 | 4.1 | 21 | 2.5
Hepatic ALT increase | 33 | 3.1 | 30 | <1
Albumin decrease | 27 | <1 | 35 | <1
AST increase | 24 | 1.5 | 19 | <1
Bilirubin increase | 16 | 1 | 13 | 2
ALP increase | 12 | 0 | 16 | <1
The denominator used to calculate the rate varied from 91 to 201 based on the number of patients with at least one post-treatment value.
a. Includes one fatal anemia.

XPOVIO in Combination with Dexamethasone (Xd)

The safety of XPOVIO in combination with dexamethasone was evaluated in STORM [see Clinical Studies (14.1)]. Patients received XPOVIO 80 mg orally with dexamethasone 20 mg on Days 1 and 3 of every week (n=202). The median duration of XPOVIO treatment was 8 weeks (range: 1 to 60 weeks). The median dose was 115 mg (range: 36 to 200 mg) per week.

Fatal adverse reactions occurred in 9% of XPOVIO treated patients. Serious adverse reactions occurred in 58% of patients.

The treatment discontinuation rate due to adverse reactions was 27%; 53% of patients had a reduction in the XPOVIO dose, and 65% had the dose of XPOVIO interrupted. Thrombocytopenia was the leading cause of dose modification, resulting in dose reduction and/or interruption in >25% of patients. The most frequent adverse reactions requiring permanent discontinuation in 4% or greater of patients who received XPOVIO included fatigue, nausea, and thrombocytopenia.

Table 9 summarizes the adverse reactions in STORM.

Table 9: Adverse Reactions (≥10%) in Patients Who Received XPOVIO in STORM
Adverse Reaction | XPOVIO 80 mg twice weekly + Dexamethasone (n=202)
Adverse Reaction | All Grades (%) | Grades ≥3 (%)
Thrombocytopeniaa | 74 | 61
Fatigueb | 73 | 22
Nausea | 72 | 9
Anemiac | 59 | 40
Decreased appetite | 53 | 4.5
Weight decreased | 47 | 0.5
Diarrhea | 44 | 6
Vomiting | 41 | 3.5
Hyponatremia | 39 | 22
Neutropeniad | 34 | 21
Leukopenia | 28 | 11
Constipation | 25 | 1.5
Dyspneae | 24 | 3.5k
Upper respiratory tract infectionf | 21 | 3
Coughg | 16 | 0
Mental status changesh | 16 | 7
Pyrexia | 16 | 0.5
Hyperglycemia | 15 | 7
Dizziness | 15 | 0
Insomnia | 15 | 2
Lymphopenia | 15 | 10
Dehydration | 14 | 3.5
Hypercreatininemiai | 14 | 2
Pneumoniaj | 13 | 9k
Epistaxis | 12 | 0.5
Hypokalemia | 12 | 3.5
Dysgeusia | 11 | 0
Vision blurred | 10 | 0.5
Headache | 10 | 0
a. Thrombocytopenia includes thrombocytopenia and platelet count decreased.
b. Fatigue includes fatigue and asthenia.
c. Anemia includes anemia and hematocrit decreased.
d. Neutropenia includes neutropenia and neutrophil count decreased.
e. Dyspnea includes dyspnea, dyspnea exertional, and dyspnea at rest.
f. Upper respiratory tract infection includes upper respiratory tract infection, respiratory tract infection, pharyngitis, nasopharyngitis, bronchitis, bronchiolitis, respiratory syncytial virus infection, parainfluenza virus infection, rhinitis, rhinovirus infection, and adenovirus infection.
g. Cough includes cough, productive cough, and upper-airway cough syndrome.
h. Mental status changes includes mental status changes, confusional state, and delirium.
i. Hypercreatininemia includes hypercreatininemia and hypercreatinemia.
j. Pneumonia includes pneumonia, atypical pneumonia, lung infection, lower respiratory tract infection, pneumocystis jirovecii pneumonia, pneumonia aspiration, pneumonia influenzal, and pneumonia viral.
k. Includes fatal event.

Diffuse Large B-Cell Lymphoma

The safety of XPOVIO was evaluated in SADAL [see Clinical Studies (14.2)]. Patients received XPOVIO 60 mg orally on Days 1 and 3 of every week (n=134). The study required an absolute neutrophil count ≥1000/μL, platelet count ≥75,000/μL, hepatic transaminases ≤2.5 times upper limit of normal (ULN) unless abnormal from lymphoma, and bilirubin ≤2 times ULN. The study permitted a maximum of 5 prior systemic regimens for DLBCL. Antiemetic prophylaxis with a 5HT-3 receptor antagonist was required. The median duration of XPOVIO treatment was 2.1 months (range: 1 week to 3.7 years) with 38% receiving at least 3 months and 22% receiving at least 6 months of treatment. The median exposure was 100 mg per week.

Fatal adverse reactions occurred in 3.7% of patients within 30 days and 5% of patients within 60 days of last treatment; the most frequent fatal adverse reaction was infection (4.5% of patients). Serious adverse reactions occurred in 46% of patients who received XPOVIO; the most frequent serious adverse reaction was infection (21% of patients).

Discontinuation due to adverse reactions occurred in 17% of patients who received XPOVIO. Adverse reactions which results in discontinuation in ≥2% of patients included: infection, fatigue, thrombocytopenia, and nausea.

Adverse reactions led to XPOVIO dose interruption in 61% of patients and dose reduction in 49%, with 17% of all patients having 2 or more dose reductions. The median time to first dose modification (reduction or interruption) was 4 weeks, with the leading causes being thrombocytopenia (40% of all patients), neutropenia (16%), fatigue (16%), nausea (10%), and anemia (10%). The median time to first dose reduction was 6 weeks, with 83% of first dose reductions occurring within the first 3 months.

The most common adverse reactions, excluding laboratory abnormalities, in ≥20% of patients were fatigue, nausea, diarrhea, decreased appetite, weight decreased, constipation, vomiting, and pyrexia. Table 10 summarizes selected adverse reactions in SADAL.

Table 10: Adverse Reactions (≥10%), Excluding Laboratory Terms, in Patients with DLBCL Who Received XPOVIO in SADAL
Adverse Reaction | XPOVIO 60 mg twice weekly (n=134)
Adverse Reaction | All Grades (%) | Grade 3 or 4 (%)
General Conditions Fatiguea | 63 | 15
Pyrexia | 22 | 4.5
Edemab | 17 | 2.2
Gastrointestinal Nausea | 57 | 6
Diarrheac | 37 | 3.0
Constipation | 29 | 0
Vomiting | 28 | 1.5
Abdominal paind | 10 | 0
Adverse Reaction | XPOVIO 60 mg twice weekly (n=134)
Adverse Reaction | All Grades (%) | Grade 3 or 4 (%)
Metabolism and Nutrition Decreased appetitee | 37 | 3.7
Weight decreased | 30 | 0
Respiratory Coughf | 18 | 0
Dyspneag | 10 | 1.5
Infections Upper respiratory tract infectionh | 17 | 1.5
Pneumonia | 10 | 6
Urinary tract infectioni | 10 | 3
Nervous System Dizzinessj | 16 | 0.7
Taste disorderk | 13 | 0
Mental status changesl | 11 | 3.7
Peripheral neuropathy, sensorym | 10 | 0
Musculoskeletal Musculoskeletal painn | 15 | 2.2
Vascular Hypotension | 13 | 3.0
Hemorrhageo | 10 | 0.7
Eye Disorders Vision blurredp | 11 | 0.7
a. Fatigue includes fatigue and asthenia.
b. Edema includes edema, swelling, swelling face, edema peripheral, peripheral swelling, acute pulmonary edema.
c. Diarrhea includes diarrhea, post-procedural diarrhea, gastroenteritis.
d. Abdominal pain includes abdominal pain, abdominal pain upper, abdominal discomfort, epigastric discomfort.
e. Decreased appetite includes decreased appetite and hypophagia.
f. Cough includes cough and productive cough.
g. Dyspnea includes dyspnea and dyspnea exertional.
h. Upper respiratory tract infection includes upper respiratory tract infection, sinusitis, nasopharyngitis, pharyngitis, rhinitis, viral upper respiratory infection.
i. Urinary tract infection includes urinary tract infection and specific types of urinary tract infection.
j. Dizziness includes dizziness and vertigo.
k. Taste disorder includes taste disorder, dysgeusia, ageusia.
l. Mental status changes include confusional state, amnesia, cognitive disorder, hallucination, delirium, somnolence, depressed level of consciousness, memory impairment.
m. Peripheral neuropathy includes peripheral neuropathy, peripheral sensory neuropathy, sensory disturbance, paresthesia, neuralgia.
n. Musculoskeletal pain includes musculoskeletal pain, back pain, musculoskeletal chest pain, neck pain, pain in extremity, bone pain.
o. Hemorrhage includes hemorrhage, hematoma, hematuria, epistaxis, rectal hemorrhage, injection site hematoma, subdural hematoma, upper gastrointestinal hemorrhage, corneal bleeding.
p. Vision blurred includes vision blurred, visual acuity reduced, visual impairment.

Clinically relevant adverse reactions in <10% of patients who received XPOVIO included:

- Injury: fall (8%)
- Metabolic and nutrition disorders: dehydration (7%)
- Neurologic disorders: headache (4.5%), syncope (2.2%)
- Infection: sepsis (6%), herpes virus infection (3%)
- Eye disorders: cataract (3.7%)
- Blood and lymphatic disorders: febrile neutropenia (3%)
- Cardiac disorders: cardiac failure (3%)

Table 11 summarizes selected new or worsening laboratory abnormalities in SADAL. Grade 3-4 laboratory abnormalities in ≥15% included thrombocytopenia, lymphopenia, neutropenia, anemia, and hyponatremia. Grade 4 laboratory abnormalities in ≥5% were thrombocytopenia (18%), lymphopenia (5%), and neutropenia (9%).

Table 11: Select Laboratory Abnormalities (≥15%) Worsening from Baseline in Patients with DLBCL Who Received XPOVIO in SADAL
Laboratory Abnormality | XPOVIO 60 mg twice weekly
Laboratory Abnormality | All Grades (%) | Grade 3 or 4 (%)
Hematologic Platelet count decrease | 86 | 49
Hemoglobin decrease | 82 | 25
Lymphocyte count decrease | 63 | 37
Neutrophil count decrease | 58 | 31
Chemistry Sodium decrease | 62 | 16
Glucose increase | 57a | 5
Creatinine increase | 47 | 3.9
Phosphate decrease | 34 | 11
Magnesium decrease | 30 | 2.6
Calcium decrease | 30 | 0.9
Potassium increase | 26 | 3.9
Potassium decrease | 23 | 7
CK increaseb | 21 | 1.9
Hepatic ALT increase | 29 | 0.8
Albumin decrease | 25 | 0
AST increase | 24 | 3.1
Bilirubin increase | 16 | 1.6
The denominator used to calculate the rate varied from 107 to 128 based on the number of patients with at least one post-treatment value.
a. Not fasting.
b. CK increase was not associated with reports of myopathy or myalgia.

8 USE IN SPECIFIC POPULATIONS

8.1 Pregnancy

Risk Summary

Based on findings in animal studies and its mechanism of action [see Clinical Pharmacology (12.1)], XPOVIO can cause fetal harm when administered to a pregnant woman. There are no available data in pregnant women to inform the drug-associated risk. In animal reproduction studies, administration of selinexor to pregnant rats during organogenesis resulted in structural abnormalities and alterations to growth at exposures that were below those occurring clinically at the recommended dose (see Data). Advise pregnant women of the risks to a fetus.

The estimated background risk of major birth defects and miscarriage for the indicated population is unknown. All pregnancies have a background risk of birth defect, loss, or other adverse outcomes. In the U.S. general population, the estimated background risk of major birth defects and miscarriage in clinically recognized pregnancies is 2% to 4% and 15% to 20%, respectively.

Data

Animal data

In an embryo-fetal development study in pregnant rats, daily oral administration of selinexor at 0, 0.25, 0.75, or 2 mg/kg throughout organogenesis caused incomplete or delayed ossification, skeletal variations, and reduced fetal weight compared with controls at a dose of 0.75 mg/kg (approximately 0.08-fold of human area under the curve [AUC] at the recommended dose). Malformations were observed at 2 mg/kg, including microphthalmia, fetal edema, malpositioned kidney, and persistent truncus arteriosus.

8.2 Lactation

Risk Summary

There is no information regarding the presence of selinexor or its metabolites in human milk, or their effects on the breastfed child or milk production. Because of the potential for serious adverse reactions in a breastfed child, advise women not to breastfeed during treatment with XPOVIO and for 1 week after the last dose.

8.3 Females and Males of Reproductive Potential

XPOVIO can cause fetal harm when administered to a pregnant woman [see Use in Specific Populations (8.1)].

Pregnancy Testing

Verify the pregnancy status of females of reproductive potential prior to initiating XPOVIO [see Use in Specific Populations (8.1)].

Contraception

Females

Advise females of reproductive potential to use effective contraception during treatment with XPOVIO and for 1 week after the last dose.

Males

Advise males with a female partner of reproductive potential to use effective contraception during treatment with XPOVIO and for 1 week after the last dose.

Infertility

Females and Males

Based on findings in animals, XPOVIO may impair fertility in females and males of reproductive potential [see Nonclinical Toxicology (13.1)].

8.4 Pediatric Use

The safety and effectiveness of XPOVIO have not been established in pediatric patients.

8.5 Geriatric Use

In BOSTON, of the 195 patients with multiple myeloma who received XPOVIO in combination with bortezomib and dexamethasone, 56% were 65 years of age and older, while 17% were 75 years of age and older. No overall differences in effectiveness were observed between these patients and younger patients. When comparing patients 65 years of age and older to younger patients, older patients had a higher incidence of discontinuation due to an adverse reaction (28% vs 13%) and a higher incidence of serious adverse reactions (56% vs 47%).

In STORM, of the 202 patients with multiple myeloma who received XPOVIO, 49% were 65 years of age and older, while 11% were 75 years of age and older. No overall difference in effectiveness was observed in patients over 65 years of age, including patients over 75 years of age, when compared with younger patients. When comparing patients 75 years of age and older to younger patients, older patients had a higher incidence of discontinuation due to an adverse reaction (44% vs 27%), higher incidence of serious adverse reactions (70% vs 58%), and higher incidence of fatal adverse reactions (17% vs 9%).

Among 134 patients with DLBCL who received XPOVIO in SADAL, 61% were 65 years of age and older, while 25% were 75 years of age and older. Clinical studies of XPOVIO in patients with relapsed or refractory DLBCL did not include sufficient numbers of patients aged 65 and over to determine whether they respond differently from younger patients.

8.6 Hepatic Impairment

No dose adjustment for selinexor is required for mild (total bilirubin ≤1x ULN and AST >1x ULN, or total bilirubin >1.0 to 1.5x ULN and any AST) or moderate (total bilirubin >1.5x to 3.0x ULN, and any AST) hepatic impairment. Reduce the starting dose in patients with severe (total bilirubin >3.0x ULN, and any AST) hepatic impairment [see Dosage and Administration (2.6) and Clinical Pharmacology (12.3)].

11 DESCRIPTION

Selinexor is a nuclear export inhibitor. Selinexor is (2Z)-3-{3-[3,5-bis(trifluoromethyl)phenyl]-1H-1,2,4-triazol-1yl}-N'-(pyrazin-2-yl)prop-2-enehydrazide. It is a white to off-white powder and has the molecular formula C17H11F6N7O and a molecular mass of 443.31 g/mol. The molecular structure is shown below:

XPOVIO tablets for oral dosing are supplied in six strengths, with each tablet containing 10 mg, 20 mg, 40 mg, 50 mg, 60 mg, or 80 mg of selinexor as the active ingredient. The inactive ingredients are colloidal silicon dioxide, croscarmellose sodium, magnesium stearate, microcrystalline cellulose, Opadry 200 clear, Opadry II blue, povidone K30, and sodium lauryl sulfate.

12 CLINICAL PHARMACOLOGY

12.1 Mechanism of Action

In nonclinical studies, selinexor reversibly inhibits nuclear export of tumor suppressor proteins (TSPs), growth regulators, and mRNAs of oncogenic proteins by blocking exportin 1 (XPO1). XPO1 inhibition by selinexor leads to accumulation of TSPs in the nucleus and reductions in several oncoproteins, such as c-myc and cyclin D1, cell cycle arrest, and apoptosis of cancer cells. Selinexor demonstrated pro-apoptotic activity in vitro in multiple myeloma cells and showed anti-tumor activity in murine xenograft models of multiple myeloma and diffuse large B cell lymphoma. The combination of selinexor and dexamethasone or bortezomib demonstrated synergistic cytotoxic effects in multiple myeloma in vitro and increased anti-tumor activity in murine xenograft multiple myeloma models in vivo, including those resistant to proteasome inhibitors.

12.2 Pharmacodynamics

An increase in selinexor exposure was associated with an increase in the probability of dose modification and some adverse reactions.

Cardiac Electrophysiology

The effect of multiple doses of XPOVIO, up to 175 mg per dose (1.75 times the maximum approved recommended dose), on the QTc interval was evaluated in patients with heavily pretreated hematologic malignancies. XPOVIO had no large effect (i.e. no greater than 20 ms) on QTc interval at the therapeutic dose level.

12.3 Pharmacokinetics

Selinexor Cmax and AUC increased proportionally over a dose range from 3 mg/m^2 to 85 mg/m^2 (0.05 to 1.44) times the maximum approved recommended dose, based on 1.7 m^2 body surface area. No clinically relevant accumulation at steady state was observed. Selinexor Cmax and AUC0-INF after administration of a single dose of XPOVIO in patients with hematologic malignancies are presented in Table 12.

Table 12: Selinexor Cmax and AUC After Administration of a Single Dose of XPOVIO
Mean (SD) |  | XPOVIO Dose
Mean (SD) | 60 mg | 80 mg | 100 mg
Cmax (ng/mL) | 442 (188) | 680 (124) | 693 (201)
AUC0-INF (ng·h/mL) | 4,096 (1,185) | 5,386 (1,116) | 6,998 (818)

Absorption

The Cmax is reached within 4 hours following oral administration of XPOVIO.

Effect of Food

Concomitant administration of a high-fat meal (800 to 1,000 calories with approximately 50% of total caloric content of the meal from fat) did not affect the pharmacokinetics of selinexor to a clinically significant extent.

Distribution

The apparent volume of distribution of selinexor is 133 L in patients with cancer. The protein binding of selinexor is 95%.

Elimination

Following a single dose of XPOVIO, the mean half-life is 6 to 8 hours. The apparent total clearance of selinexor is 18.6 L/h in patients with cancer.

Metabolism

Selinexor is metabolized by CYP3A4, multiple UDP-glucuronosyltransferases (UGTs) and glutathione Stransferases (GSTs).

Specific Populations

No clinically significant differences in the pharmacokinetics of selinexor were observed based on age (18 to 94 years old), sex, body weight (36 to 168 kg), ethnicity, mild to severe renal impairment (CLCR: 15 to 89 mL/min, estimated by the Cockcroft-Gault equation), and disease type (hematological non-DLBCL, solid tumor, DLBCL). The effect of end-stage renal disease (CLCR <15 mL/min) or hemodialysis on selinexor pharmacokinetics is unknown.

Patients with Hepatic Impairment

In patients with mild (total bilirubin ≤1x ULN and AST >1x ULN, or total bilirubin >1 to 1.5x ULN and any AST) or moderate (total bilirubin >1.5 to 3x ULN and any AST, n=7) hepatic impairment the pharmacokinetics of selinexor was comparable to patients with normal hepatic function (total bilirubin and AST <ULN).

In patients with severe hepatic impairment (total bilirubin >3 ULN and any AST, n=6) there was approximately 32% increase in total and free selinexor exposure compared to patients with normal hepatic function [see Dosage and Administration (2.6) and Use in Specific Populations (8.6)].

Drug Interaction Studies

Clinical Studies

Acetaminophen: No clinically significant differences in selinexor pharmacokinetics were observed when co-administered with acetaminophen (up to 1,000 mg daily dose of acetaminophen).

Clarithromycin (a strong CYP3A4 inhibitor): No clinically significant differences in selinexor pharmacokinetics were observed when co-administered with clarithromycin (up to 1,000 mg daily dose of clarithromycin).

Carbamazepine (a strong CYP3A4 inducer): No clinically significant differences in selinexor pharmacokinetics were observed when co-administered with carbamazepine (up to 300 mg twice-daily dose of carbamazepine).

In vitro Studies

CYP Enzymes: Selinexor does not inhibit CYP1A2, CYP2B6, CYP2C8, CYP2C9, CYP2C19, or CYP3A4/5. Selinexor is not a CYP3A4, CYP1A2, or CYP2B6 inducer.

Non-CYP Enzyme Systems: Selinexor is a substrate of UGTs and GSTs.

Transporter Systems: Selinexor inhibits OATP1B3 but does not inhibit other solute carrier (SLC) transporters.

Selinexor is not a substrate of P-gp, BCRP, OATP1B1, OATP1B3, OAT1, OAT3, OCT1, OCT2, MATE1, or MATE2-K.

13 NONCLINICAL TOXICOLOGY

13.1 Carcinogenesis, Mutagenesis, Impairment of Fertility

Carcinogenicity studies have not been conducted with selinexor.

Selinexor was not mutagenic in vitro in a bacterial reverse mutation (Ames) assay and was not clastogenic in either the in vitro cytogenetic assay in human lymphocytes or in the in vivo rat micronucleus assay.

Fertility studies in animals have not been conducted with selinexor. In repeat-dose oral toxicity studies, selinexor was administered for up to 13 weeks in rats and monkeys. Reduced sperm, spermatids, and germ cells in epididymides and testes were observed in rats at ≥1 mg/kg, decreased ovarian follicles were observed in rats at ≥2 mg/kg, and single cell necrosis of testes was observed in monkeys at ≥1.5 mg/kg. These dose levels resulted in systemic exposures approximately 0.11, 0.28, and 0.53 times, respectively, the exposure (AUClast) in humans at the recommended human dose of 80 mg.

14 CLINICAL STUDIES

14.1 Relapsed or Refractory Multiple Myeloma

XPOVIO Combination with Bortezomib and Dexamethasone (XVd)

The efficacy of XPOVIO in combination with bortezomib and dexamethasone was evaluated in BOSTON (NCT03110562). BOSTON was a global, randomized, open label, active-controlled trial in adult patients who had received 1 to 3 prior anti-MM regimens. Prior treatment with bortezomib or other PI was allowed.

Patients with Grade 2 or higher peripheral neuropathy at study entry were excluded.

Patients were randomized to receive one of the following:

- XPOVIO 100 mg orally once weekly on Days 1, 8, 15, 22, 29 in combination with bortezomib 1.3 mg/m^2 administered subcutaneously once weekly on Days 1, 8, 15, 22 and dexamethasone 20 mg taken orally twice weekly on Days 1, 2, 8, 9, 15, 16, 22, 23, 29, and 30 of each 35-day cycle [XVd arm] or
- Bortezomib 1.3 mg/m^2 administered subcutaneously twice weekly on Days 1, 4, 8, 11 and dexamethasone 20 mg taken orally four times weekly on Days 1, 2, 4, 5, 8, 9, 11, 12 of each 21-day cycle for the first 8 cycles, followed by bortezomib 1.3 mg/m^2 administered subcutaneously once weekly on Days 1, 8, 15, 22 and dexamethasone 20 mg taken orally twice weekly on Days 1, 2, 8, 9, 15, 16, 22, 23, 29, and 30 of each 35-day cycle (Cycle ≥9) [Vd arm].

Treatment continued in both arms until disease progression or unacceptable toxicity. Randomization was stratified based on prior proteasome inhibitor therapies exposure (yes versus no), number of prior regimens (1 versus >1), Stage (III versus I or II) according to the Revised-International Staging System (RISS) and region. Upon confirmed progressive disease (PD), patients in the Vd arm could receive XPOVIO in combination with bortezomib and dexamethasone (XVd) or XPOVIO 100 mg taken orally on Days 1, 8, 15, 22, 29 with dexamethasone 20 mg taken orally on Days 1, 2, 8, 9, 15, 16, 22, 23, 29, and 30 of each 35-day cycle.

A total of 402 patients were randomized: 195 to XVd arm and 207 to Vd arm. Baseline patient demographics and disease characteristics are summarized in Table 13 and Table 14, respectively.

Table 13: Baseline Demographics (BOSTON)
Characteristic | XVd (n=195) | Vd (n=207)
Median age, years (range) | 66 (40, 87) | 67 (38, 90)
Age distribution, n (%) <65 years | 86 (44) | 75 (36)
65 – 74 years | 75 (38) | 85 (41)
≥75 years | 34 (17) | 47 (23)
Sex, n (%) Male | 115 (59) | 115 (56)
Female | 80 (41) | 92 (44)
Race, n (%) White | 161 (83) | 165 (80)
Black or African American | 4 (2) | 7 (3)
Asian | 25 (13) | 25 (12)
Other | 0 | 1 (0.5)
Missing | 5 (3) | 9 (4)

Table 14: Disease Characteristics (BOSTON)
Parameter | XVd (n=195) | Vd (n=207)
Median years from diagnosis to randomization (range) | 3.81 (0.4, 23.0) | 3.59 (0.4, 22.0)
ECOG performance status score, n (%) 0-1 | 175 (90) | 191 (92)
≥2 | 20 (10) | 16 (8)
Creatinine Clearance, n (%), mL per minute <30 | 3 (1.5) | 10 (5)
30 to 59 | 53 (27) | 60 (29)
≥60 | 139 (71) | 137 (66)
Revised International Staging System at Baseline, n (%) I | 56 (29) | 52 (25)
II | 117 (60) | 125 (60)
III | 12 (6) | 16 (8)
Unknown | 10 (5) | 14 (7)
Number of Prior Therapies, n (%) 1 2 3 | 99 (51) 65 (33) 31 (16) | 99 (48) 64 (31) 44 (21)
Type of known prior therapy, n (%) Stem Cell transplantation | 76 (39) | 63 (30)
Lenalidomide | 77 (39) | 77 (37)
Pomalidomide | 11 (6) | 7 (3)
Bortezomib | 134 (69) | 145 (70)
Carfilzomib | 20 (10) | 21 (10)
Daratumumab | 11 (6) | 6 (3)
Median weeks since end of last prior therapy, (range) | 48 (1, 1088) | 42 (2, 405)
Known high-risk cytogeneticsa, n (%) | 97 (50) | 95 (46)
a. Includes any of del(17p)/p53, t(14;16), t(4;14), 1q21.

Efficacy was based on progression free survival (PFS) according to the International Myeloma Working Group (IMWG) Uniform Response Criteria for Multiple Myeloma, as assessed by an Independent Review Committee (IRC). Efficacy results based on a preplanned PFS interim analysis, are shown in Table 15 and Figure 1.

Table 15: Efficacy Results per IRC in Multiple Myeloma (BOSTON)
 | XVd (n=195) | Vd (n=207)
Progression Free Survival (PFS) a Hazard Ratio [95% CI] | 0.70 [0.53, 0.93]
One-sided p-valueb | 0.0075
Median PFS in months [95% CI] | 13.9 (11.7, Not Reached) | 9.5 (7.6, 10.8)
Overall Response Rate (ORR) c, n (%) | 149 (76.4) | 129 (62.3)
95% CI | (69.8, 82.2) | (55.3, 68.9)
One-sided p-value | 0.0012
Stringent Complete Response (sCR) | 19 (10) | 13 (6)
Complete Response (CR) | 14 (7) | 9 (4)
Very Good Partial Response (VGPR) | 54 (28) | 45 (22)
Partial Response (PR) | 62 (32) | 62 (30)
≥ VGPR Response Rated, n (%) | 87 (44.6) | 67 (32.4)
95% CI | (37.5, 51.9) | (26.0, 39.2)
One-sided p-value | 0.0082
a. Hazard ratio is based on stratified Cox's proportional hazard regression modeling, p-value based on stratified log-rank test.
Median follow up of 15.1 months at the time of the analysis.
b. The pre-planned PFS interim analysis boundary of statistical significance was defined as a p-value <0.0103.
c. Includes sCR + CR + VGPR + PR, p value based on Cochran-Mantel-Haenszel test.
d. Includes sCR + CR + VGPR, p value based on Cochran-Mantel-Haenszel test.

Figure 1: Kaplan-Meier Curve of PFS (BOSTON)

The median time to response was 1.4 months in the XVd arm and 1.6 months in the Vd arm. The median duration of response, among responding patients, was 20.3 months and 12.9 months in the XVd and Vd arms, respectively.

XPOVIO Combination with Dexamethasone (Xd)

The efficacy of XPOVIO plus dexamethasone was evaluated in STORM (KCP-330-012; NCT02336815). STORM was a multicenter, single-arm, open-label study of adults with relapsed or refractory multiple myeloma (RRMM). STORM Part 2 included 122 patients with RRMM who had previously received three or more antimyeloma treatment regimens including an alkylating agent, glucocorticoids, bortezomib, carfilzomib, lenalidomide, pomalidomide, and an anti-CD38 monoclonal antibody; and whose myeloma was documented to be refractory to glucocorticoids, a proteasome inhibitor, an immunomodulatory agent, an anti-CD38 monoclonal antibody, and to the last line of therapy.

In STORM Part 2, a total of 122 patients received XPOVIO 80 mg orally in combination with dexamethasone 20 mg orally on Days 1 and 3 of every week. Treatment continued until disease progression or unacceptable toxicity. Eighty-three patients had RRMM that was refractory to bortezomib, carfilzomib, lenalidomide, pomalidomide, and daratumumab. Baseline patient demographics and disease characteristics of these 83 patients are summarized in Table 16 and Table 17, respectively.

Efficacy was based on overall response rate (ORR), as assessed by an Independent Review Committee (IRC) based on the International Myeloma Working Group (IMWG) Uniform Response Criteria for Multiple

Myeloma. The approval of XPOVIO was based upon the efficacy and safety in a prespecified subgroup analysis of the 83 patients whose disease was refractory to bortezomib, carfilzomib, lenalidomide, pomalidomide, and daratumumab, as the benefit-risk ratio appeared to be greater in this more heavily pretreated population than in the overall trial population. Overall response rate results are presented in Table 18. The median time to first response was 4 weeks (range: 1 to 10 weeks). The median duration of response was 3.8 months (95% CI: 2.3, not estimable).

Table 16: Baseline Demographics (STORM)
Demographic | STORM (n=83)
Median age, years (range) | 65 (40, 86)
Age category, n (%)
<65 years | 40 (48)
65 – 74 years | 31 (37)
≥75 years | 12 (15)
Sex, n (%)
Male | 51 (61)
Female | 32 (39)
Race, n (%)
White | 58 (70)
Black or African American | 13 (16)
Asian | 2 (2)
Native Hawaiian or other Pacific Islander | 1 (1)
Other | 6 (7)
Missing | 3 (4)

Table 17: Disease Characteristics (STORM)
Parameter | STORM (n=83)
Median years from diagnosis to start of study treatment (range) | 7 (1, 23)
Prior treatment regimens, median (range) | 8 (4, 18)
Documented refractory status, n (%) Lenalidomide | 83 (100)
Pomalidomide | 83 (100)
Bortezomib | 83 (100)
Carfilzomib | 83 (100)
Daratumumab | 83 (100)
Documented refractory status to specific combinations, n (%) Bortezomib, carfilzomib, lenalidomide, pomalidomide, and daratumumab | 83 (100)
Daratumumab in any combination | 57 (69)
Daratumumab as single agent (+/- dexamethasone) | 26 (31)
Previous stem cell transplant, n (%) | 67 (81)
Revised International Staging System at Baseline, n (%) I | 10 (12)
II | 56 (68)
III | 17 (21)
Unknown | 0
High-risk cytogeneticsa, n (%) | 47 (57)
a. Includes any of del(17p)/p53, t(14; 16), t(4; 14), 1q21.

Table 18: Efficacy Results per IRC in Relapsed or Refractory Multiple Myeloma (STORM)
Response | STORM (n=83)
Overall Response Rate (ORR) a, n (%) | 21 (25.3)
95% CI | 16.4, 36
Stringent Complete Response (sCR) | 1 (1)
Complete Response (CR) | 0
Very Good Partial Response (VGPR) | 4 (5)
Partial Response (PR) | 16 (19)
a. Includes sCR + CR + VGPR + PR.

14.2 Relapsed or Refractory Diffuse Large B-Cell Lymphoma

The efficacy of XPOVIO monotherapy was evaluated in SADAL (KCP-330-009; NCT02227251). SADAL was a multicenter, single-arm, open-label study of adults with relapsed or refractory DLBCL, not otherwise specified (NOS), after 2 to 5 systemic regimens. Eligible patients were not candidates for autologous hematopoietic stem cell transplantation (HSCT). The study required a minimum of 60 days since last systemic therapy, with a minimum of 98 days in patients with refractory disease (defined as less than partial response) to last systemic therapy.

Patients received XPOVIO 60 mg orally on Days 1 and 3 of each week. Treatment continued until disease progression or unacceptable toxicity. Of 134 patients evaluated, the median age was 67 years (range: 35-91), 59% were male, 79% were White, and 7% were Asian. Most patients (88%) had an ECOG performance status of 0 or 1. The diagnosis was de novo DLBCL not otherwise specified (NOS) in 75% and transformed DLBCL in 23%. The median number of prior systemic therapies was 2 (range: 1-5), with 63% of patients receiving 2 prior systemic therapies, 24% receiving 3 prior therapies, and 10% receiving 4 or 5 prior therapies. Twenty-eight percent had documented refractory disease to the most recent therapy; 30% had prior autologous HSCT. The median time from last systemic therapy to the start of XPOVIO was 5.4 months overall and 3.6 months in the patients with refractory disease.

Efficacy was based on overall response rate (ORR) and duration of response as assessed by an Independent Review Committee (IRC) using Lugano 2014 criteria (Table 19). The median time to first response was 8.1 weeks (range: 6.7-16.4 weeks).

Table 19: Efficacy Results per IRC in Relapsed or Refractory DLBCL (SADAL)
Parameter | XPOVIO 60 mg twice weekly (n=134)
ORR per Lugano criteria, n (%) 95% CI, % | 39 (29) 22, 38
Complete Response | 18 (13)
Partial Response | 21 (16)
Duration of Response Patients maintaining response at 3 months, n/N (%) | 22/39 (56)
Patients maintaining response at 6 months, n/N (%) | 15/39 (38)
Patients maintaining response at 12 months, n/N (%) | 6/39 (15)

16 HOW SUPPLIED/STORAGE AND HANDLING

XPOVIO 10 mg tablets are blue, round, bi-convex, film-coated debossed with “X10” on one side and nothing on the other side.

XPOVIO 20 mg tablets are blue, round, bi-convex, film-coated debossed with “K20” on one side and nothing on the other side.

XPOVIO 40 mg tablets are blue, oval, film-coated, debossed on both sides with “X40”.

XPOVIO 50 mg tablets are blue, oval, film-coated, debossed on both sides with “X50”.

XPOVIO 60 mg tablets are blue, oval, film-coated, debossed on both sides with “X60”.

XPOVIO 80 mg tablets are blue, oval, film-coated, debossed on both sides with “X80”.

Tablets are packaged in a child-resistant blister pack. Four blister packs are supplied per carton. The following nine dose presentations are available:

Weekly dose | Strength per tablet | Carton (28-day supply) | Blister Pack | NDC
100 mg once weekly | 50 mg | 4 blister packs (8 tablets total in the carton) | Each blister has two 50 mg tablets | Outer carton NDC 72237-103-05 Blister pack NDC 72237-103-15
80 mg once weekly | 40 mg | 4 blister packs (8 tablets total in the carton) | Each blister has two 40 mg tablets | Outer carton NDC 72237-102-02 Blister pack NDC 72237-102-12
80 mg once weekly | 80 mg | 4 blister packs (4 tablets total in the carton) | Each blister has one 80 mg tablet | Outer carton NDC 72237-105-01 Blister pack NDC 72237-105-11
60 mg once weekly | 60 mg | 4 blister packs (4 tablets total in the carton) | Each blister has one 60 mg tablet | Outer carton NDC 72237-104-01 Blister pack NDC 72237-104-11
40 mg once weekly | 10 mg | 4 blister packs (16 tablets total in the carton) | Each blister has four 10 mg tablets | Outer carton NDC 72237-106-01 Blister pack NDC 72237-106-11
40 mg once weekly | 40 mg | 4 blister packs (4 tablets total in the carton) | Each blister has one 40 mg tablet | Outer carton NDC 72237-102-07 Blister pack NDC 72237-102-17
80 mg twice weekly | 20 mg | 4 blister packs (32 tablets total in the carton) | Each blister has eight 20 mg tablets | Outer carton NDC 72237-101-04 Blister pack NDC 72237-101-14
60 mg twice weekly | 20 mg | 4 blister packs (24 tablets total in the carton) | Each blister has six 20 mg tablets | Outer carton NDC 72237-101-03 Blister pack NDC 72237-101-13
40 mg twice weekly | 40 mg | 4 blister packs (8 tablets total in the carton) | Each blister has two 40 mg tablets | Outer carton NDC 72237-102-06 Blister pack NDC 72237-102-16

Store at or below 30°C (86°F).

17 PATIENT COUNSELING INFORMATION

Advise the patient to read the FDA-approved patient labeling (Medication Guide).

Dosing Instructions [see Dosage and Administration (2)]:

- Instruct patients to take XPOVIO exactly as prescribed.
- Advise patients to swallow the tablet whole with water. The tablet should not be broken, chewed, crushed, or divided.
- If a patient misses a dose, advise them to take their next dose at its regularly scheduled time. If a patient vomits or misses a dose of XPOVIO, advise them to take the next dose on the next regularly scheduled day.
- Advise patients that XPOVIO comes in a child-resistant blister pack.
- Advise patients to take their prescribed dexamethasone (if applicable) and prophylactic anti-nausea medications as directed [see Dosage and Administration (2.1, 2.3)].
- Advise patients that blood tests and body weight will be monitored at baseline and during treatment as clinically indicated, with more frequent monitoring during the first three months of treatment [see Dosage and Administration (2.3)].
- Advise patients to maintain appropriate fluid and caloric intake throughout their treatment [see Dosage and Administration (2.4)].

Hematologic Adverse Reactions

Thrombocytopenia

Advise patients that they may develop low platelet counts (thrombocytopenia). Symptoms of thrombocytopenia may include bleeding and easy bruising. Advise patients that platelet counts will be monitored at baseline, during treatment, and as clinically indicated, with more frequent monitoring during the first 3 months of treatment. Advise patients to report signs of bleeding right away [see Warnings and Precautions (5.1)].

Anemia

Advise patients that they may develop anemia. Symptoms of anemia may include fatigue and shortness of breath. Advise patients to report signs or symptoms of anemia [see Adverse Reactions (6.1)].

Neutropenia

Advise patients that they may develop low neutrophil counts which may increase their susceptibility to infection [see Warnings and Precautions (5.2)]. Advise patients that neutrophil counts will be monitored at baseline, during treatment, and as clinically indicated, with more frequent monitoring during the first 3 months of treatment.

Gastrointestinal Adverse Reactions

Advise patients they may experience nausea/vomiting or diarrhea and to contact their physician if these adverse reactions occur or persist [see Warnings and Precautions (5.3)].

Advise patients that they may experience weight loss or decreased appetite. Advise patients to report decreased appetite and weight loss [see Warnings and Precautions (5.3)].

Hyponatremia

Advise patients that they may develop low sodium levels (hyponatremia). Most cases of hyponatremia were not associated with specific symptoms. Advise patients that levels of sodium will be monitored at baseline and during treatment as clinically indicated, with more frequent monitoring during the first two months of treatment [see Warnings and Precautions (5.4)].

Serious Infection

Advise patients of the possibility of serious infections. Instruct patients to immediately report infection-related signs or symptoms (e.g., chills, fever) [see Warnings and Precautions (5.5)].

Neurotoxicity

Advise patients that they may experience confusion and dizziness. Advise patients to report symptoms of neurological toxicity right away. Advise patients not to drive or operate hazardous machinery until the neurological toxicity fully resolves. Advise patients to use fall prevention measures as warranted [see Warnings and Precautions (5.6)].

Embryo-Fetal Toxicity

Advise pregnant women of the potential risk to a fetus. Advise females of reproductive potential to contact their healthcare provider of a known or suspected pregnancy [see Warnings and Precautions (5.7) and Use in Specific Populations (8.1)].

Advise females of reproductive potential and males with a female partner of reproductive potential to use effective contraception during treatment with XPOVIO and for 1 week after the final dose [see Use in Specific Populations (8.3)].

Cataract

Advise patients of the potential risk of worsening or new onset of cataract, that may require surgery. Advise patients to readily inform their healthcare professionals of changes in vision (i.e. blurred vision) and that ophthalmologic evaluation may be performed as clinically indicated [see Warnings and Precautions (5.8)].

Fatigue

Advise patients that they may experience fatigue [see Adverse Reactions (6.1)].

Lactation

Advise women not to breastfeed during treatment with XPOVIO and for 1 week after the last dose [see Use in Specific Populations (8.2)].

Concomitant Medications

Advise patients to take 5-HT3 antagonist prophylactic treatment and other anti-nausea agents prior to and during treatment with XPOVIO [see Dosage and Administration (2.4)].

Advise patients to speak with their physician about other medications they are currently taking and before starting any new medication.

Manufactured for and marketed by: Karyopharm Therapeutics Inc., 85 Wells Avenue, Newton, MA, 02459.
XPOVIO is a registered trademark of Karyopharm Therapeutics Inc.
©2025 Karyopharm Therapeutics Inc.
For more information, call 1-888-209-9326 or go to www.XPOVIO.com.

MEDICATION GUIDE
XPOVIO® (x-PO-Vee-O)
(selinexor) tablets

What is the most important information I should know about XPOVIO? XPOVIO can cause serious side effects, including:
Low platelet counts and low white blood cell counts are common with XPOVIO and can sometimes be severe or life-threatening.

- Low platelet counts. Low platelet counts can lead to bleeding which can sometimes cause death. Your healthcare provider may prescribe platelet transfusions or other treatments for your low platelet counts.
  Tell your healthcare provider right away if you have any bleeding or easy bruising during treatment with XPOVIO.
- Low white blood cell counts. You may have an increased risk of infection during treatment with XPOVIO. Tell your healthcare provider if you have any signs or symptoms of infection, including fever, chills, cough, shortness of breath, pain during urination, or feeling generally unwell. Your healthcare provider may prescribe antibiotics, or certain medicines to help increase your white blood cell count, if needed.

Your healthcare provider will do blood tests before you start taking XPOVIO and often during the first 3 months of treatment and then as needed during treatment to monitor your blood cell counts.
See “What are the possible side effects of XPOVIO?” for more information about side effects.

What is XPOVIO?
XPOVIO is a prescription medicine used:

- in combination with the medicines bortezomib and dexamethasone to treat adults with multiple myeloma (MM) who have received at least one prior treatment for their disease.
- in combination with dexamethasone to treat adults with multiple myeloma (MM) that has come back (relapsed) or that did not respond to previous treatment (refractory), and
  - who have received at least 4 prior therapies, and
  - whose disease did not respond to (refractory) to at least 2 proteasome inhibitor medicines, at least 2 immunomodulatory agents, and an anti-CD38 monoclonal antibody medicine.
- to treat adults with certain types of diffuse large B-cell lymphoma (DLBCL) that has come back (relapsed) or that did not respond to previous treatment (refractory) and who have received at least 2 prior therapies.

It is not known if XPOVIO is safe and effective in children.

Before taking XPOVIO, tell your healthcare provider about all of your medical conditions, including if you:

- have or have had a recent or active infection
- have or have had bleeding problems
- have or have had liver problems
- have cataracts
- are pregnant or plan to become pregnant. XPOVIO can harm your unborn baby.
  Females who are able to become pregnant:
  - Your healthcare provider will check to see if you are pregnant before you start taking XPOVIO.
  - You should use effective birth control (contraception) during treatment with XPOVIO and for 1 week after your last dose.
  - Tell your healthcare provider right away if you become pregnant or think you might be pregnant during treatment with XPOVIO.
  Males with female partners who are able to become pregnant:
  - You should use effective birth control (contraception) during treatment with XPOVIO and for 1 week after your last dose.
- are breastfeeding or plan to breastfeed. It is not known if XPOVIO passes into your breast milk. Do not breastfeed during treatment with XPOVIO and for 1 week after your last dose of XPOVIO.

Tell your healthcare provider about all the medicines you take, including prescription and over-the-counter medicines, vitamins, and herbal supplements. Talk with your healthcare provider before taking any new medicines.

How should I take XPOVIO?

- Take XPOVIO exactly as prescribed by your healthcare provider. Do not change your dose or stop taking XPOVIO without talking to your healthcare provider first.
- If you have multiple myeloma, your healthcare provider will prescribe dexamethasone with your XPOVIO treatment. Take dexamethasone exactly as prescribed.
- Swallow XPOVIO tablets whole with water. Do not break, chew, crush, or divide the tablets.
- Take any medicines your healthcare provider prescribes before and during treatment with XPOVIO to help prevent nausea and vomiting. Tell your healthcare provider if the prescribed medicine does not help your nausea and vomiting.
- It is important for you to drink enough fluids to help prevent dehydration and to eat enough calories to help prevent weight loss during treatment with XPOVIO. Talk to your healthcare provider if this is a problem for you. See “What are the possible side effects of XPOVIO?”
- If you miss a dose of XPOVIO, take your next dose at your next regularly scheduled day and time.
- If you vomit after taking a dose of XPOVIO, do not take an extra dose. Take your next dose at your next regularly scheduled day and time.

What should I avoid while taking XPOVIO?
XPOVIO can cause neurologic side effects.

- See “What are the possible side effects of XPOVIO?” below.
- If you have any neurologic side effects with XPOVIO, do not drive or operate heavy or dangerous machinery until your neurologic side effects go away.
- Avoid falling. Use care as needed to avoid falling due to neurologic side effects.

What are the possible side effects of XPOVIO?

XPOVIO can cause serious side effects, including:

- See “What is the most important information I should know about XPOVIO?”
- Stomach and intestinal (gastrointestinal) problems are common with XPOVIO and can sometimes be severe.
  - Nausea and vomiting. Nausea and vomiting may affect your ability to eat and drink well. You can lose too much body fluid and body salts (electrolytes) and may be at risk for becoming dehydrated. You may need to receive intravenous (IV) fluids or other treatments to help prevent dehydration. Your healthcare provider will prescribe anti-nausea medicines for you to take before you start and during treatment with XPOVIO. See “How should I take XPOVIO?”
  - Diarrhea. You can lose too much body fluid and body salts (electrolytes) and may be at risk for becoming dehydrated. You may need to receive IV fluids or other treatments to help prevent dehydration. Your healthcare provider will prescribe anti-diarrhea medicine for you as needed.
  - Loss of appetite and weight loss. Tell your healthcare provider if you have a decrease or loss of appetite and if you notice that you are losing weight at any time during treatment. Your healthcare provider may prescribe medicines that can help increase your appetite or prescribe other kinds of nutritional support. Your healthcare provider will monitor your appetite and weight before you start XPOVIO and often during the first 3 months, then as needed during treatment.
- Decreased sodium levels in your blood. Decreased sodium levels in your blood is common with XPOVIO but can also sometimes be severe or life-threatening. Low sodium levels in your blood can happen if you have nausea, vomiting, or diarrhea, you become dehydrated, or if you have loss of appetite with XPOVIO. You may not have any symptoms of a low sodium level. Your healthcare provider may talk with you about your diet and prescribe IV fluids for you based on the sodium levels in your blood. Your healthcare provider will do blood tests before you start taking XPOVIO, and often during the first 2 months of treatment, and then as needed during treatment to monitor the sodium levels in your blood.
- Serious infections. XPOVIO can cause infections that can sometimes cause death, including upper or lower respiratory tract infections, such as pneumonia, and an infection throughout your body (sepsis). Tell your healthcare provider right away if you have any signs or symptoms of an infection such as cough, chills or fever, during treatment with XPOVIO.
- Neurologic side effects. XPOVIO can cause neurologic side effects that can sometimes be severe and life- threatening.
  - XPOVIO can cause dizziness, fainting, decreased alertness, and changes in your mental status including confusion and decreased awareness of things around you (delirium).
  - In some people, XPOVIO may also cause problems with thinking (cognitive problems), seeing or hearing things that are not really there (hallucinations), and may become very sleepy or drowsy.
  - Taking other medicines that can cause dizziness or mental status changes during treatment with XPOVIO may increase your risk of neurologic side effects. Talk to your healthcare provider about all of your medicines.
  Tell your healthcare provider right away if you get any of these signs or symptoms.
- New or worsening cataract, a cloudy or loss of transparency of the lens in the eye. New or worsening cataract are common with XPOVIO. If a cataract forms, your vision may decrease, and you may need eye surgery to remove the cataract and restore your vision. Tell your healthcare provider right away if you have symptoms of a cataract such as double vision, blurred vision, sensitivity to light or glare.

Your healthcare provider may change your dose of XPOVIO, stop your treatment for a period of time, or completely stop your treatment if you have certain side effects during treatment with XPOVIO.

The most common side effects of XPOVIO in adults with multiple myeloma in combination with bortezomib and dexamethasone include:

- tiredness
- numbness, tingling, or burning in your hands or feet (peripheral neuropathy)

- upper respiratory tract infection
- low phosphate levels in your blood
- low red blood cell count (anemia). Symptoms may include tiredness and shortness of breath.

The most common side effects of XPOVIO in adults with multiple myeloma in combination with dexamethasone include:

- tiredness
- low red blood cell count (anemia). Symptoms may include tiredness and shortness of breath.

- constipation
- shortness of breath
- upper respiratory tract infection

The most common side effects of XPOVIO in adults with DLBCL include:

- tiredness
- constipation
- fever

- low red blood cell count (anemia). Symptoms may include tiredness and shortness of breath.

XPOVIO may cause fertility problems in males and females, which may affect your ability to have children. Talk to your healthcare provider if you have concerns about fertility.
These are not all the possible side effects of XPOVIO.
Call your doctor for medical advice about side effects. You may report side effects to FDA at 1-800-FDA-1088.

How should I store XPOVIO?

- Store XPOVIO at or below 86°F (30°C).
- XPOVIO comes in a child-resistant blister pack.

Keep XPOVIO and all medicines out of the reach of children.

General information about the safe and effective use of XPOVIO.
Medicines are sometimes prescribed for purposes other than those listed in a Medication Guide. Do not use XPOVIO for a condition for which it was not prescribed. Do not give XPOVIO to other people, even if they have the same symptoms that you have. It may harm them. You can ask your pharmacist or healthcare provider for information about
XPOVIO that is written for health professionals.

What are the ingredients in XPOVIO? Active ingredient: selinexor
Inactive ingredients: colloidal silicon dioxide, croscarmellose sodium, magnesium stearate, microcrystalline cellulose,
Opadry 200 clear, Opadry II blue, povidone K30, and sodium lauryl sulfate.
Manufactured for and marketed by: Karyopharm Therapeutics Inc., 85 Wells Avenue, Newton, MA, 02459
XPOVIO is a registered trademark of Karyopharm Therapeutics Inc. All other trademarks are the property of their respective owners.
©2025 Karyopharm Therapeutics Inc.
For more information, call 1-888-209-9326 or go to www.XPOVIO.com

This Medication Guide has been approved by the U.S. Food and Drug Administration.

Revised: 9/2025

Principal Display Panel – 40 mg (Once Weekly) Carton Label

NDC 72237-106-01

Rx ONLY

40 mg
Once
Weekly
Blister Packs

XPOVIO®

(selinexor) tablets

Contents: 4 individual weekly
blister packs. Each blister pack
contains 4 tablets (10 mg per tablet).

16 film-coated tablets

Dispense enclosed Medication Guide
to each patient.

Karyopharm®
Therapeutics

Principal Display Panel – 40 mg (Once Weekly) Blister Sleeve Label

NDC 72237-106-11

Rx ONLY

1 PRESS
& HOLD
HERE

40 mg
Once
Weekly
Blister Pack

1. PRESS 2. PULL

XPOVIO®

(selinexor) tablets

TO OPEN

Step 1: Press and
hold button gently.

Step 2: Pull out
medication card.

Blister pack contains
4 tablets (10 mg per tablet).

Refer to Prescribing
Information for dosing
instructions.

Do not break, chew, crush,
or divide the tablets.

Dispense enclosed Medication
Guide to each patient.

Karyopharm®
Therapeutics

Principal Display Panel – 40 mg (Once Weekly) Blister Pack Label

XPOVIO®(selinexor) tablets

40 mg Dose
(entire pack)

IMPORTANT:
Take each dose as prescribed
by your physician. Take only
one 40 mg dose in a single
day per week. Refer to
Prescribing Information for
dosing instructions.

Push tablets through foil.

Swallow whole with water.

Principal Display Panel – 60 mg (Twice Weekly) Carton Label

NDC 72237-101-03

Rx ONLY

60 mg
Twice
Weekly
Blister Packs

(120 mg total weekly dose)

XPOVIO®

(selinexor) tablets

Contents: 4 individual weekly
blister packs. Each blister pack
contains 6 tablets (20 mg per tablet).

24 film-coated tablets

Dispense enclosed Medication Guide
to each patient.

Karyopharm®
Therapeutics

Principal Display Panel – 60 mg (Twice Weekly) Blister Sleeve Label

NDC 72237-101-13

Rx ONLY

1 PRESS
& HOLD
HERE

60 mg
Twice
Weekly
Blister Pack

(120 mg total weekly dose)

1. PRESS 2. PULL

XPOVIO®

(selinexor) tablets

TO OPEN

Step 1: Press and
hold button gently.

Step 2: Pull out
medication card.

Blister pack contains
6 tablets (20 mg per tablet).

Refer to Prescribing
Information for dosing
instructions.

Do not break, chew, crush,

or divide the tablets.

Dispense enclosed Medication
Guide to each patient.

Karyopharm®
Therapeutics

Principal Display Panel – 60 mg (Twice Weekly) Blister Pack Label

XPOVIO®(selinexor) tablets

60 mg
Dose
(entire pack)

Push tablets
through foil.

Swallow
whole with
water.

IMPORTANT: Take each dose as prescribed by your physician.

Take only one 60 mg dose in a single day. Take one 60 mg dose on Day 1 and one 60 mg dose on Day 3 of the week.

Refer to Prescribing Information for dosing instructions.

Principal Display Panel – 80 mg (Twice Weekly) Carton Label

NDC 72237-101-04

Rx ONLY

80 mg
Twice
Weekly
Blister Packs

(160 mg total weekly dose)

XPOVIO®

(selinexor) tablets

Contents: 4 individual weekly
blister packs. Each blister pack
contains 8 tablets (20 mg per tablet).

32 film-coated tablets

Dispense enclosed Medication Guide
to each patient.

Karyopharm®
Therapeutics

Principal Display Panel – 80 mg (Twice Weekly) Blister Sleeve Label

NDC 72237-101-14

Rx ONLY

1 PRESS
& HOLD
HERE

80 mg
Twice
Weekly
Blister Pack

(160 mg total weekly dose)

1.PRESS 2. PULL

XPOVIO®

(selinexor) tablets

TO OPEN

Step 1: Press and
hold button gently.

Step 2: Pull out
medication card.

Blister pack contains
8 tablets (20 mg per tablet).

Refer to Prescribing
Information for dosing
instructions.

Do not break, chew, crush,
or divide the tablets.

Dispense enclosed Medication
Guide to each patient.

Karyopharm®
Therapeutics

Principal Display Panel – 80 mg (twice Weekly) Blister Pack Label

XPOVIO®(selinexor) tablets

80 mg
Dose
(entire pack)

Push tablets
through foil.

Swallow
whole with
water.

IMPORTANT: Take each dose as prescribed by your physician.

Take only one 80 mg dose in a single day. Take one 80 mg dose on Day 1 and one 80 mg dose on Day 3 of the week.

Refer to Prescribing Information for dosing instructions.

Principal Display Panel – 40 mg (Once Weekly) Carton Label

NDC 72237-102-07

Rx ONLY

40 mg
Once
Weekly
Blister Packs

XPOVIO®

(selinexor) tablets

Contents: 4 individual weekly blister packs. Each blister pack contains 1 tablet (40 mg per tablet).

4 film-coated tablets

Dispense enclosed Medication Guide to each patient

Karyopharm®
Therapeutics

Principal Display Panel – 40 mg (Once Weekly) Blister Sleeve Label

NDC 72237-102-17

Rx ONLY

1 PRESS
& HOLD
HERE

40 mg
Once
Weekly
Blister Pack

1. PRESS 2. PULL

XPOVIO®

(selinexor) tablets

TO OPEN

Step 1: Press and
hold button gently.

Step 2: Pull out
medication card.

Blister pack contains
1 tablet (40 mg per tablet).

Refer to Prescribing
Information for dosing
instructions.

Do not break, chew, crush,
or divide the tablets.

Dispense enclosed Medication
Guide to each patient.

Karyopharm®
Therapeutics

Principal Display Panel – 40 mg (Once Weekly) Blister Pack Label

XPOVIO®(selinexor)tablets

40 mg Dose
40
mg

IMPORTANT: Take each dose as prescribed by your physician.

Take only one 40 mg dose in a single day per week.

Refer to Prescribing Information for dosing instructions.

Push tablet through foil.

Swallow whole with water.

Principal Display Panel – 40 mg (Twice Weekly) Carton Label

NDC 72237-102-06

Rx ONLY

40 mg
Twice
Weekly
Blister Packs

(80 mg total
weekly dose)

XPOVIO®

(selinexor) tablets

Contents: 4 individual weekly blister packs. Each blister pack contains 2 tablets (40 mg per tablet).

8 film-coated tablets

Dispense enclosed Medication Guide to each patient

Karyopharm®
Therapeutics

Principal Display Panel – 40 mg (Twice Weekly) Blister Sleeve Label

NDC 72237-102-16

Rx ONLY

1 PRESS
& HOLD
HERE

40 mg
Twice
Weekly
Blister Pack

(80 mg total
weekly dose)

1. PRESS 2. PULL

XPOVIO®

(selinexor) tablets

TO OPEN

Step 1: Press and
hold button gently.

Step 2: Pull out
medication card.

Blister pack contains
2 tablets (40 mg per tablet).

Refer to Prescribing
Information for dosing
instructions.

Do not break, chew, crush,
or divide the tablets.

Dispense enclosed Medication
Guide to each patient.

Karyopharm®
Therapeutics

Principal Display Panel – 40 mg (Twice Weekly) Blister Pack Label

XPOVIO®(selinexor) tablets

40
mg

40 mg
Dose

IMPORTANT: Take each dose as prescribed by your physician.

Take only one 40 mg dose in a single day.

Take one 40 mg dose on Day 1 and one 40 mg dose on Day 3 of the week.

Refer to Prescribing Information for dosing instructions.

Push tablet through foil.

Swallow whole with water.

Principal Display Panel – 60 mg (Once Weekly) Carton Label

NDC 72237-104-01

Rx ONLY

60 mg
Once
Weekly
Blister Packs

XPOVIO®

(selinexor) tablets

Contents: 4 individual weekly blister packs. Each blister pack contains 1 tablet (60 mg per tablet).

4 film-coated tablets

Dispense enclosed Medication Guide to each patient

Karyopharm®
Therapeutics

Principal Display Panel – 60 mg (Once Weekly) Blister Sleeve Label

NDC 72237-104-11

Rx ONLY

1 PRESS
& HOLD
HERE

60 mg
Once
Weekly
Blister Pack

1. PRESS 2. PULL

XPOVIO®

(selinexor) tablets

TO OPEN

Step 1: Press and
hold button gently.

Step 2: Pull out
medication card.

Blister pack contains
1 tablet (60 mg per tablet).

Refer to Prescribing
Information for dosing
instructions.

Do not break, chew, crush,
or divide the tablets.

Dispense enclosed Medication
Guide to each patient.

Karyopharm®
Therapeutics

Principal Display Panel – 60 mg (Once Weekly) Blister Pack Label

XPOVIO®(selinexor) tablets

60 mg Dose
60
mg

IMPORTANT: Take each dose as prescribed by your physician.

Take only one 60 mg dose in a single day per week.

Refer to Prescribing Information for dosing instructions.

Push tablet through foil.

Swallow whole with water.

Principal Display Panel – 80 mg (Once Weekly) Carton Label

NDC 72237-102-02

Rx ONLY

80 mg
Once
Weekly
Blister Packs

XPOVIO®

(selinexor) tablets

Contents: 4 individual weekly blister packs. Each blister pack contains 2 tablets (40 mg per tablet).

8 film-coated tablets

Dispense enclosed Medication Guide to each patient

Karyopharm®
Therapeutics

Principal Display Panel – 80 mg (Once Weekly) Blister Sleeve Label

NDC 72237-102-12

Rx ONLY

1 PRESS
& HOLD
HERE

80 mg
Once
Weekly
Blister Pack

1. PRESS 2. PULL

XPOVIO®

(selinexor) tablets

TO OPEN

Step 1: Press and
hold button gently.

Step 2: Pull out
medication card.

Blister pack contains
2 tablets (40 mg per tablet).

Refer to Prescribing
Information for dosing
instructions.

Do not break, chew, crush,
or divide the tablets.

Dispense enclosed Medication
Guide to each patient.

Karyopharm®
Therapeutics

Principal Display Panel – 80 mg (Once Weekly) Blister Pack Label

XPOVIO®(selinexor) tablets

80 mg Dose
(entire pack)
40
mg

40
mg

IMPORTANT: Take each dose as prescribed by your physician.

Take only one 80 mg dose in a single day per week.

Refer to Prescribing Information for dosing instructions.

Push tablet through foil.

Swallow whole with water.

PACKAGE LABEL

Principal Display Panel – 80 mg (Once Weekly) Carton Label

NDC 72237-105-01

Rx ONLY

80 mg
Once
Weekly
Blister Packs

XPOVIO®

(selinexor) tablets

Contents: 4 individual weekly
blister packs. Each blister pack
contains 1 tablet (80 mg per tablet).

4 film-coated tablets

Dispense enclosed Medication Guide
to each patient.

Karyopharm®
Therapeutics

PACKAGE LABEL

Principal Display Panel – 80 mg (Once Weekly) Blister Sleeve Label

NDC 72237-105-11

Rx ONLY

1 PRESS
& HOLD
HERE

80 mg
Once
Weekly
Blister Pack

1. PRESS 2. PULL

XPOVIO®

(selinexor) tablets

TO OPEN

Step 1: Press and
hold button gently.

Step 2: Pull out
medication card.

Blister pack contains
1 tablet (80 mg per tablet).

Refer to Prescribing
Information for dosing
instructions.

Do not break, chew, crush,
or divide the tablets.

Dispense enclosed Medication
Guide to each patient.

Karyopharm®
Therapeutics

PACKAGE LABEL

Principal Display Panel – 80 mg (Once Weekly) Blister Pack Label

XPOVIO®(selinexor) tablets

80 mg Dose
80
mg

IMPORTANT:
Take each dose as prescribed
by your physician. Take only
one 80 mg dose in a single
day per week. Refer to
Prescribing Information for
dosing instructions.

Push tablets through foil.

Swallow whole with water.

Principal Display Panel – 100 mg (Once Weekly) Carton Label

NDC 72237-103-05

Rx ONLY

100 mg
Once
Weekly
Blister Packs

XPOVIO®

(selinexor) tablets

Contents: 4 individual weekly blister packs. Each blister pack contains 2 tablets (50 mg per tablet).

8 film-coated tablets

Dispense enclosed Medication Guide to each patient

Karyopharm®
Therapeutics

Principal Display Panel – 100 mg (Once Weekly) Blister Sleeve Label

NDC 72237-103-15

Rx ONLY

1 PRESS
& HOLD
HERE

100 mg
Once
Weekly
Blister Pack

1. PRESS 2. PULL

XPOVIO®

(selinexor) tablets

TO OPEN

Step 1: Press and
hold button gently.

Step 2: Pull out
medication card.

Blister pack contains
2 tablets (50 mg per tablet).

Refer to Prescribing
Information for dosing
instructions.

Do not break, chew, crush,
or divide the tablets.

Dispense enclosed Medication
Guide to each patient.

Karyopharm®
Therapeutics

Principal Display Panel – 100 mg (Once Weekly) Blister Pack Label

XPOVIO®(selinexor) tablets

100 mg Dose
(entire pack)
50
mg

50
mg

IMPORTANT: Take each dose as prescribed by your physician.

Take only one 100 mg dose in a single day per week.

Refer to Prescribing Information for dosing instructions.

Push tablet through foil.

Swallow whole with water.